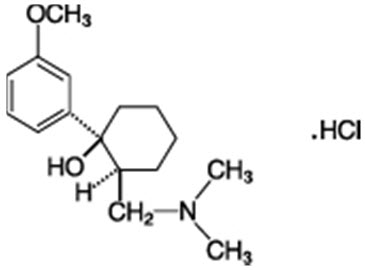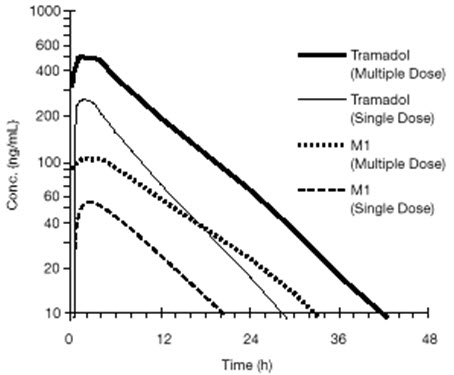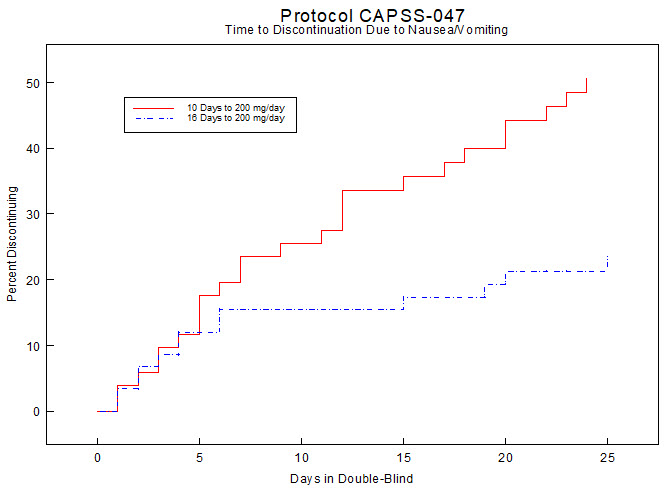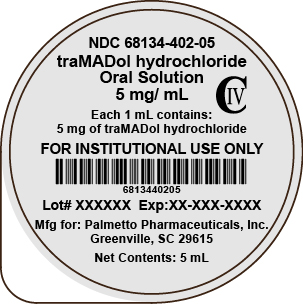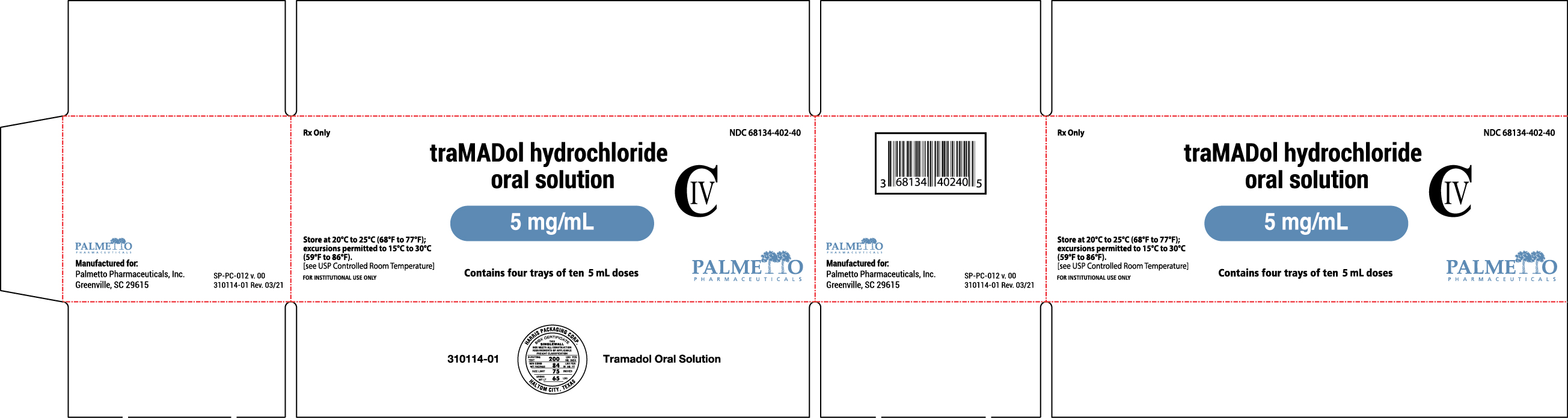 DRUG LABEL: tramadol hydrochloride
NDC: 68134-402 | Form: SOLUTION
Manufacturer: Palmetto Pharmaceuticals, Inc.
Category: prescription | Type: HUMAN PRESCRIPTION DRUG LABEL
Date: 20241209
DEA Schedule: CIV

ACTIVE INGREDIENTS: TRAMADOL HYDROCHLORIDE 5 mg/1 mL
INACTIVE INGREDIENTS: CITRIC ACID MONOHYDRATE; GLYCERIN; PROPYLENE GLYCOL; SODIUM BENZOATE; TRISODIUM CITRATE DIHYDRATE; SUCRALOSE; WATER

HIGHLIGHTS OF PRESCRIBING INFORMATION

These highlights do not include all the information needed to use TRAMADOL HYDROCHLORIDE ORAL SOLUTION safely and effectively. See full prescribing information for TRAMADOL HYDROCHLORIDE ORAL SOLUTION.
TRAMADOL HYDROCHLORIDE oral solution C-IV
Initial U.S. Approval: 1995

WARNING: SERIOUS AND LIFE-THREATENING RISKS FROM USE OF TRAMADOL HYDROCHLORIDE ORAL SOLUTION

See full prescribing information for complete boxed warning.

- Ensure accuracy when prescribing, dispensing, and administering tramadol hydrochloride oral solution. Dosing errors due to confusion between mg and mL can result in accidental overdose and death. (2.1, 5.1)
- Tramadol hydrochloride oral solution exposes users to the risks of addiction, abuse and misuse, which can lead to overdose and death. Assess each patient's risk prior to prescribing tramadol hydrochloride oral solution, and reassess regularly for these behaviors or conditions. (5.2)
- Serious, life-threatening, or fatal respiratory depression may occur, especially during initiation or following a dosage increase. To reduce the risk of respiratory depression, proper dosing and titration of tramadol hydrochloride oral solution are essential. (5.3)
- Accidental ingestion of tramadol hydrochloride oral solution, especially by children, can result in a fatal overdose of tramadol. (5.3)
- Concomitant use of opioids with benzodiazepines or other central nervous system (CNS) depressants, including alcohol, may result in profound sedation, respiratory depression, coma, and death. Reserve concomitant prescribing for use in patients for whom alternative treatment options are inadequate. (5.4, 7)
- If opioid use is required for an extended period of time in a pregnant woman, advise the patient of the risk of Neonatal Opioid Withdrawal Syndrome, which may be life-threatening if not recognized and treated. Ensure that management by neonatology experts will be available at delivery. (5.5)
- Life-threatening respiratory depression and death have occurred in children who received tramadol. Some of the reported cases followed tonsillectomy and/or adenoidectomy; in at least one case, the child had evidence of being an ultra-rapid metabolizer of tramadol due to a CYP2D6 polymorphism (5.7).
- Healthcare providers are strongly encouraged to complete a REMS-compliant education program and to counsel patients and caregivers on serious risks, safe use, and the importance of reading the Medication Guide with each prescription. (5.6)
- Tramadol hydrochloride oral solution is contraindicated in children younger than 12 years of age and in children younger than 18 years of age following tonsillectomy and/or adenoidectomy (4). Avoid the use of tramadol hydrochloride oral solution in adolescents 12 to 18 years of age who have other risk factors that may increase their sensitivity to the respiratory depressant effects of tramadol. (5.7)
- The effects of concomitant use or discontinuation of cytochrome P450 3A4 inducers, 3A4 inhibitors, or 2D6 inhibitors with tramadol are complex. Use of cytochrome P450 3A4 inducers, 3A4 inhibitors, or 2D6 inhibitors with tramadol hydrochloride oral solution requires careful consideration of the effects on the parent drug, tramadol, and the active metabolite, M1. (5.8, 7)

RECENT MAJOR CHANGES

Boxed Warnings | 12/2023
Indications and Usage (1) | 12/2023
Dosage and Administration (2.1), (2.3), (2.4) | 12/2023
Warnings and Precautions (5.9) | 12/2023

1 INDICATIONS AND USAGE

Tramadol hydrochloride oral solution is an opioid agonist indicated in adults for the management of pain severe enough to require an opioid analgesic and for which alternative treatments are inadequate (1).

Limitations of Use(1)
Because of the risks of addiction, abuse, and misuse with opioids, which can occur at any dosage or duration (5.2), reserve tramadol hydrochloride oral solution for use in patients for whom alternative treatment options [e.g., non-opioid analgesics]:

- Have not been tolerated or are not expected to be tolerated.
- Have not provided adequate analgesia or are not expected to provide adequate analgesia.

Tramadol hydrochloride oral solution should not be used for an extended period of time unless the pain remains severe enough to require an opioid analgesic and for which alternative treatment options continue to be inadequate.

2 DOSAGE AND ADMINISTRATION

- Tramadol hydrochloride oral solution should be prescribed only by healthcare professionals who are knowledgeable about the use of opioids and how to mitigate the associated risks. (2.1)
- Use the lowest effective dosage for the shortest duration consistent with individual patient treatment goals. Reserve titration to higher doses of tramadol hydrochloride oral solution for patients in whom lower doses are insufficiently effective and in whom the expected benefits of using a higher dose opioid clearly outweigh the substantial risks. (2.1, 5)
- Many acute pain conditions (e.g., the pain that occurs with a number of surgical procedures or acute musculoskeletal injuries) require no more than a few days of an opioid analgesic. Clinical guidelines on opioid prescribing for some acute pain conditions are available. (2.1)
- Initiate the dosing regimen for each patient individually, taking into account the patient’s underlying cause and severity of pain, prior analgesic treatment and response, and risk factors for addiction, abuse, and misuse. (2.1, 5.2)
- Respiratory depression can occur at any time during opioid therapy, especially when initiating and following dosage increases with tramadol hydrochloride oral solution. Consider this risk when selecting an initial dose and when making dose adjustments. (2.1, 5.3)
- Discuss availability of naloxone with the patient and caregiver and assess each patient’s need for access to naloxone, both when initiating and renewing treatment with tramadol hydrochloride oral solution. Consider prescribing naloxone based on the patient’s risk factors for overdose (2.2, 5.2, 5.3, 5.4).
- Start at 25 mg /day and titrate in 25 mg increments as separate doses every 3 days to reach 100 mg /day (25 mg four times a day). Thereafter the total daily dose may be increased by 50 mg as tolerated every 3 days to reach 200 mg /day (50 mg four times a day). After titration, tramadol hydrochloride oral solution 50 mg to 100 mg can be administered as needed for pain relief every 4 to 6 hours not to exceed 400 mg /day(2.3, 2.4).
- Severe hepatic impairment: Recommended dose is 50 mg every 12 hours (2.3).
- Do not abruptly discontinue tramadol hydrochloride oral solution in a physically-dependent patient because rapid discontinuation of opioid analgesics has resulted in serious withdrawal symptoms, uncontrolled pain, and suicide (2.5).

3 DOSAGE FORMS AND STRENGTHS

- Oral Solution: tramadol hydrochloride 5 mg/mL (3).

4 CONTRAINDICATIONS

- Children younger than 12 years of age (4).
- Postoperative management in children younger than 18 years of age following tonsillectomy and/or adenoidectomy (4).
- Significant respiratory depression (4).
- Acute or severe bronchial asthma in an unmonitored setting or in the absence of resuscitative equipment (4).
- Known or suspected gastrointestinal obstruction, including paralytic ileus (4).
- Hypersensitivity to tramadol, any other component of this product or opioids (4).
- Concurrent use of monoamine oxidase inhibitors (MAOIs) or use of MAOIs within the last 14 days (4).

5 WARNINGS AND PRECAUTIONS

- Opioid-Induced Hyperalgesia and Allodynia:Opioid-Induced Hyperalgesia (OIH) occurs when an opioid analgesic paradoxically causes an increase in pain, or an increase in sensitivity to pain. If OIH is suspected, carefully consider appropriately decreasing the dose of the current opioid analgesic or opioid rotation. (5.9)
- Serotonin Syndrome:May be life-threatening. Can occur with use of tramadol alone, with concomitant use of serotonergic drugs, with drugs that impair metabolism of serotonin or tramadol (5.10).
- Risk of Seizure:Can occur at the recommended dose of tramadol. Concomitant use with other drugs may increase seizure risk. Risk may increase in patients with epilepsy, a history of seizures, and in patients with a recognized risk for seizures (5.11).
- Risk of Suicide:Do not prescribe for suicidal or addiction-prone patients (5.12).
- Life-Threatening Respiratory Depression in Patients with Chronic Pulmonary Disease or in Elderly, Cachectic, or Debilitated Patients:Regularly evaluate closely, particularly during initiation and titration (5.13).
- Adrenal Insufficiency:If diagnosed, treat with physiologic replacement of corticosteroids, and wean patient off the opioid (5.14).
- Severe Hypotension:Regularly evaluate during dosage initiation and titration. Avoid use of tramadol hydrochloride oral solution in patients with circulatory shock (5.15).
- Risks of Use in Patients with Increased Intracranial Pressure, Brain Tumors, Head Injury, or Impaired Consciousness: monitor for sedation and respiratory depression. Avoid use of tramadol hydrochloride oral solution in patients with impaired consciousness or coma (5.16).

6 ADVERSE REACTIONS

The most common incidence of treatment-emergent adverse events (≥15.0%) in patients from clinical trials were dizziness/vertigo, nausea, constipation, headache, somnolence, vomiting and pruritus (6).

To report SUSPECTED ADVERSE REACTIONS, contact Palmetto Pharmaceuticals, Inc. at 1-844-627-7696 or FDA at 1-800-FDA-1088 or www.fda.gov/medwatch.

7 DRUG INTERACTIONS

Mixed Agonist/Antagonist and Partial Agonist Opioid Analgesics: Avoid use with tramadol hydrochloride oral solution because they may reduce analgesic effect of tramadol hydrochloride oral solution or precipitate withdrawal symptoms (7).

8 USE IN SPECIFIC POPULATIONS

- Pregnancy:May cause fetal harm (8.1)
- Lactation:Breastfeeding not recommended (8.2)

FULL PRESCRIBING INFORMATION

WARNING: SERIOUS AND LIFE-THREATENING RISKS FROM USE OF TRAMADOL HYDROCHLORIDE ORAL SOLUTION

Risk of Medication Errors
Ensure accuracy when prescribing, dispensing, and administering tramadol hydrochloride oral solution. Dosing errors due to confusion between mg and mL can result in accidental overdose and death [see Dosage and Administration (2.1), Warnings and Precautions (5.1)].

Addiction, Abuse and Misuse
Because the use of tramadol hydrochloride oral solution exposes patients and other users to the risks of opioid addiction, abuse and misuse, which can lead to overdose and death, assess each patient's risk prior to prescribing tramadol hydrochloride oral solution and reassess all patients regularly for the development of these behaviors and conditions [see Warnings and Precautions (5.2)] .

Life-Threatening Respiratory Depression
Serious, life-threatening, or fatal respiratory depression may occur with use of tramadol hydrochloride oral solution, especially during initiation or following a dosage increase. To reduce the risk of respiratory depression, proper dosing and titration of tramadol hydrochloride oral solution are essential [see Warnings and Precautions (5.3)] .

Accidental Ingestion
Accidental ingestion of even one dose of tramadol hydrochloride oral solution, especially by children, can result in a fatal overdose of tramadol [see Warnings and Precautions (5.3)] .

Risks From Concomitant Use With Benzodiazepines Or Other CNS Depressants
Concomitant use of opioids with benzodiazepines or other central nervous system (CNS) depressants, including alcohol, may result in profound sedation, respiratory depression, coma, and death. Reserve concomitant prescribing of tramadol hydrochloride oral solution and benzodiazepines or other CNS depressants for use in patients for whom alternative treatment options are inadequate [see Warnings and Precautions (5.4), Drug Interactions (7)] .

Neonatal Opioid Withdrawal Syndrome (NOWS)
If opioid use is required for an extended period of time in a pregnant woman, advise the patient of the risk of NOWS, which may be life-threatening if not recognized and treated. Ensure that management by neonatology experts will be available at delivery [see Warnings and Precautions (5.5)] .

Opioid Analgesic Risk Evaluation and Mitigation Strategy (REMS)
Healthcare providers are strongly encouraged to complete a REMS-compliant education program and to counsel patients and caregivers on serious risks, safe use, and the importance of reading the Medication Guide with each prescription [see Warnings and Precautions (5.6)] .

Ultra-Rapid Metabolism of Tramadol and Other Risk Factors for Life-Threatening Respiratory Depression in Children
Life-threatening respiratory depression and death have occurred in children who received tramadol. Some of the reported cases followed tonsillectomy and/or adenoidectomy; in at least one case, the child had evidence of being an ultra-rapid metabolizer of tramadol due to a CYP2D6 polymorphism [see Warnings and Precautions (5.7)] . Tramadol hydrochloride oral solution is contraindicated in children younger than 12 years of age and in children younger than 18 years of age following tonsillectomy and/or adenoidectomy [see Contraindications (4)] . Avoid the use of tramadol hydrochloride oral solution in adolescents 12 to 18 years of age who have other risk factors that may increase their sensitivity to the respiratory depressant effects of tramadol [see Warnings and Precautions (5.7)] .

Interactions With Drugs Affecting Cytochrome P450 Isoenzymes
The effects of concomitant use or discontinuation of cytochrome P450 3A4 inducers, 3A4 inhibitors, or 2D6 inhibitors with tramadol are complex. Use of cytochrome P450 3A4 inducers, 3A4 inhibitors, or 2D6 inhibitors with tramadol hydrochloride oral solution requires careful consideration of the effects on the parent drug, tramadol, and the active metabolite, M1 [see Warnings and Precautions (5.8), Drug Interactions (7)] .

1 INDICATIONS AND USAGE

Tramadol hydrochloride oral solution is indicated in adults for the management of pain severe enough to require an opioid analgesic and for which alternative treatments are inadequate.

Limitations of Use
Because of the risks of addiction, abuse, and misuse with opioids, which can occur at any dosage or duration [see Warnings and Precautions (5.2)] , reserve tramadol hydrochloride oral solution for use in patients for whom alternative treatment options [e.g., non-opioid analgesics]:

- Have not been tolerated or are not expected to be tolerated.
- Have not provided adequate analgesia or are not expected to provide adequate analgesia.

Tramadol hydrochloride oral solution should not be used for an extended period of time unless the pain remains severe enough to require an opioid analgesic and for which alternative treatment options continue to be inadequate.

2 DOSAGE AND ADMINISTRATION

2.1 Important Dosage and Administration Instructions

- Ensure accuracy when prescribing, dispensing, and administering tramadol hydrochloride oral solution to avoid dosing errors due to confusion between mg and mL which could result in accidental overdose and death. Ensure the proper dose is communicated and dispensed. When writing prescriptions, include both the total dose in mg and the total dose in volume.
- Instruct patients and caregivers on how to measure and take or administer the correct dose of tramadol hydrochloride oral solution.
- Strongly advise patients and caregivers to always use a graduated oral syringe or measuring cup, with metric units of measurements (i.e., mL), to correctly measure the prescribed amount of medication.
- Inform patients that oral dosing devices may be obtained from their pharmacy and to never use household teaspoons or tablespoons to measure tramadol hydrochloride oral solution.
- Do not use tramadol hydrochloride oral solution concomitantly with other tramadol-containing products.
- Do not administer tramadol hydrochloride oral solution at a dose exceeding 400 mg (80 mL) per day.
- Tramadol hydrochloride oral solution should be prescribed only by healthcare professionals who are knowledgeable about the use of opioids and how to mitigate the associated risks.
- Use the lowest effective dosage for the shortest duration of time consistent with individual patient treatment goals [see Warnings and Precautions (5)] . Because the risk of overdose increases as opioid doses increase, reserve titration to higher doses of tramadol hydrochloride oral solution for patients in whom lower doses are insufficiently effective and in whom the expected benefits of using a higher dose opioid clearly outweigh the substantial risks.
- Many acute pain conditions (e.g., the pain that occurs with a number of surgical procedures or acute musculoskeletal injuries) require no more than a few days of an opioid analgesic. Clinical guidelines on opioid prescribing for some acute pain conditions are available.
- There is variability in the opioid analgesic dose and duration needed to adequately manage pain due both to the cause of pain and to individual patient factors. Initiate the dosing regimen for each patient individually, taking into account the patient’s underlying cause and severity of pain, prior analgesic treatment and response, and risk factors for addiction, abuse, and misuse [see Warnings and Precautions (5.2)] .
- Respiratory depression can occur at any time during opioid therapy, especially when initiating and following dosage increases with tramadol hydrochloride oral solution. Consider this risk when selecting an initial dose and when making dose adjustments [see Warnings and Precautions (5)] .

2.2 Patient Access to Naloxone for the Emergency Treatment of Opioid Overdose

Discuss the availability of naloxone for the emergency treatment of opioid overdose with the patient and caregiver and assess the potential need for access to naloxone, both when initiating and renewing treatment with tramadol hydrochloride oral solution [see Warnings and Precautions (5.3)] .

Inform patients and caregivers about the various ways to obtain naloxone as permitted by individual state naloxone dispensing and prescribing requirements or guidelines (e.g., by prescription, directly from a pharmacist, or as part of a community-based program).

Consider prescribing naloxone, based on the patient’s risk factors for overdose, such as concomitant use of CNS depressants, a history of opioid use disorder, or prior opioid overdose. The presence of risk factors for overdose should not prevent the proper management of pain in any given patient [see Warnings and Precautions (5.2, 5.3, 5.4)] .

Consider prescribing naloxone if the patient has household members (including children) or other close contacts at risk for accidental ingestion or overdose.

2.3 Initial Dosage

Initiating Treatment with Tramadol Hydrochloride Oral Solution

Initiate treatment at the lowest dose necessary to achieve adequate analgesia. Titrate the dose based upon the individual patient’s response to their initial dose of tramadol hydrochloride oral solution.

For patients not requiring rapid onset of analgesic effect, the tolerability of tramadol hydrochloride oral solution can be improved by initiating therapy with the following titration regimen: Start tramadol hydrochloride oral solution at 25 mg/day and titrate in 25 mg increments as separate doses every 3 days to reach 100 mg/day (25 mg four times a day). Thereafter the total daily dose may be increased by 50 mg as tolerated every 3 days to reach 200 mg/day (50 mg four times a day). After titration, tramadol hydrochloride oral solution 50 mg to 100 mg can be administered as needed for pain relief every 4 to 6 hours not to exceed 400 mg/day.

For the subset of patients for whom rapid onset of analgesic effect is required and for whom the benefits outweigh the risk of discontinuation due to adverse events associated with higher initial doses, tramadol hydrochloride oral solution 50 mg to 100 mg can be administered as needed for pain relief every four to six hours, not to exceed 400 mg/day.

Conversion from tramadol hydrochloride oral solution to Extended-Release Tramadol

The relative bioavailability of tramadol hydrochloride oral solution compared to extended-release tramadol is unknown, so conversion to extended-release formulations may lead to increased risk of excessive sedation and respiratory depression.

Dosage Modification in Patients with Hepatic Impairment

The recommended dose for adult patients with severe hepatic impairment is 50 mg every 12 hours.

Dosage Modification in Patients with Renal Impairment

In all patients with creatinine clearance less than 30 mL/min, it is recommended that the dosing interval of tramadol hydrochloride oral solution be increased to 12 hours, with a maximum daily dose of 200 mg. Since only 7% of an administered dose is removed by hemodialysis, dialysis patients can receive their regular dose on the day of dialysis.

Dosage Modification in Geriatric Patients

Do not exceed a total dose of 300 mg/day in patients over 75 years old.

2.4 Titration and Maintenance of Therapy

Individually titrate tramadol hydrochloride oral solution to a dose that provides adequate analgesia and minimizes adverse reactions. Continually reevaluate patients receiving tramadol hydrochloride oral solution to assess the maintenance of pain control, signs and symptoms of opioid withdrawal, and other adverse reactions, as well as to reassess for the development of addiction, abuse, or misuse [see Warnings and Precautions (5.2, 5.19)] . Frequent communication is important among the prescriber, other members of the healthcare team, the patient, and the caregiver/family during periods of changing analgesic requirements, including initial titration.

If the level of pain increases after dosage stabilization, attempt to identify the source of increased pain before increasing the tramadol hydrochloride oral solution dosage. If after increasing the dosage, unacceptable opioid-related adverse reactions are observed (including an increase in pain after dosage increase), consider reducing the dosage [see Warnings and Precautions (5)] . Adjust the dosage to obtain an appropriate balance between management of pain and opioid-related adverse reactions.

2.5 Safe Reduction or Discontinuation of Tramadol Hydrochloride Oral Solution

Do not abruptly discontinue tramadol hydrochloride oral solution in patients who may be physically dependent on opioids. Rapid discontinuation of opioid analgesics in patients who are physically dependent on opioids has resulted in serious withdrawal symptoms, uncontrolled pain, and suicide. Rapid discontinuation has also been associated with attempts to find other sources of opioid analgesics, which may be confused with drug-seeking for abuse. Patients may also attempt to treat their pain or withdrawal symptoms with illicit opioids, such as heroin, and other substances.

When a decision has been made to decrease the dose or discontinue therapy in an opioid- dependent patient taking tramadol hydrochloride oral solution, there are a variety of factors that should be considered, including the total daily dose of opioid (including tramadol hydrochloride oral solution) the patient has been taking, the duration of treatment, the type of pain being treated, and the physical and psychological attributes of the patient. It is important to ensure ongoing care of the patient and to agree on an appropriate tapering schedule and follow-up plan so that patient and provider goals and expectations are clear and realistic. When opioid analgesics are being discontinued due to a suspected substance use disorder, evaluate and treat the patient, or refer for evaluation and treatment of the substance use disorder. Treatment should include evidence-based approaches, such as medication assisted treatment of opioid use disorder. Complex patients with comorbid pain and substance use disorders may benefit from referral to a specialist.

There are no standard opioid tapering schedules that are suitable for all patients. Good clinical practice dictates a patient-specific plan to taper the dose of the opioid gradually. For patients on tramadol hydrochloride oral solution who are physically opioid-dependent, initiate the taper by a small enough increment, (e.g., no greater than 10% to 25% of the total daily dose) to avoid withdrawal symptoms, and proceed with dose-lowering at an interval of every 2 to 4 weeks. Patients who have been taking opioids for briefer periods of time may tolerate a more rapid taper.

It may be necessary to provide the patient with a lower dosage strength to accomplish a successful taper. Reassess the patient frequently to manage pain and withdrawal symptoms, should they emerge. Common withdrawal symptoms include restlessness, lacrimation, rhinorrhea, yawning, perspiration, chills, myalgia, and mydriasis. Other signs and symptoms also may develop, including irritability, anxiety, backache, joint pain, weakness, abdominal cramps, insomnia, nausea, anorexia, vomiting, diarrhea, or increased blood pressure, respiratory rate, or heart rate. If withdrawal symptoms arise, it may be necessary to pause the taper for a period of time or raise the dose of the opioid analgesic to the previous dose, and then proceed with a slower taper. In addition, evaluate patients for any changes in mood, emergence of suicidal thoughts, or use of other substances.

When managing patients taking opioid analgesics, particularly those who have been treated for an extended period of time, and/or with high doses for chronic pain, ensure that a multimodal approach to pain management, including mental health support (if needed), is in place prior to initiating an opioid analgesic taper. A multimodal approach to pain management may optimize the treatment of chronic pain, as well as assist with the successful tapering of the opioid analgesic [see Warnings and Precautions (5.19), Drug Abuse and Dependence (9.3)] .

3 DOSAGE FORMS AND STRENGTHS

Tramadol hydrochloride oral solution is supplied as a clear liquid in 16 oz white, opaque plastic bottles, containing tramadol hydrochloride, 5 mg/mL (equivalent to tramadol 4.4 mg per 1 mL).

4 CONTRAINDICATIONS

Tramadol hydrochloride oral solution is contraindicated for:

- all children younger than 12 years of age [see Warnings and Precautions (5.7)] .
- postoperative management in children younger than 18 years of age following tonsillectomy and/or adenoidectomy [see Warnings and Precautions (5.7)] .

Tramadol hydrochloride oral solution is also contraindicated in patients with:

- Significant respiratory depression [see Warnings and Precautions (5.3)] .
- Acute or severe bronchial asthma in an unmonitored setting or in the absence of resuscitative equipment [see Warnings and Precautions (5.13)] .
- Known or suspected gastrointestinal obstruction, including paralytic ileus [see Warnings and Precautions (5.17)] .
- Hypersensitivity to tramadol, any other component of this product or opioids [see Warnings and Precautions (5.18)] .
- Concurrent use of monoamine oxidase inhibitors (MAOIs) or use within the last 14 days [see Drug Interactions (7)] .

5 WARNINGS AND PRECAUTIONS

5.1 Risk of Accidental Overdose and Death due to Medication Errors

Dosing errors can result in accidental overdose and death. Avoid dosing errors that may result from confusion between mg and mL when prescribing, dispensing, and administering tramadol hydrochloride oral solution. Ensure that the dose is communicated clearly and dispensed accurately.

Instruct patients and caregivers on how to measure and take or administer the correct dose of tramadol hydrochloride oral solution and to use extreme caution when measuring the dose. Strongly advise patients and caregivers to always use a graduated device that can measure and deliver the prescribed dose accurately, and to never use household teaspoons or tablespoons to measure a dose because these are not adequate measuring devices.

5.2 Addiction, Abuse, and Misuse

Tramadol hydrochloride oral solution contains tramadol, a Schedule IV controlled substance. As an opioid, tramadol hydrochloride oral solution exposes users to the risks of addiction, abuse, and misuse [see Drug Abuse and Dependence (9)].

Although the risk of addiction in any individual is unknown, it can occur in patients appropriately prescribed tramadol hydrochloride oral solution. Addiction can occur at recommended dosages and if the drug is misused or abused.

Assess each patient's risk for opioid addiction, abuse, or misuse prior to prescribing tramadol hydrochloride oral solution, and reassess all patients receiving tramadol hydrochloride oral solution for the development of these behaviors and conditions. Risks are increased in patients with a personal or family history of substance abuse (including drug or alcohol abuse or addiction) or mental illness (e.g., major depression). The potential for these risks should not, however, prevent the proper management of pain in any given patient. Patients at increased risk may be prescribed opioids such as tramadol hydrochloride oral solution, but use in such patients necessitates intensive counseling about the risks and proper use of tramadol hydrochloride oral solution along with frequent reevaluation for signs of addiction, abuse, and misuse. Consider prescribing naloxone for the emergency treatment of opioid overdose [see Dosage and Administration (2.2), Warnings and Precautions (5.2)] .

Opioids are sought for nonmedical use and are subject to diversion from legitimate prescribed use. Consider these risks when prescribing or dispensing tramadol hydrochloride oral solution. Strategies to reduce these risks include prescribing the drug in the smallest appropriate quantity and advising the patient on careful storage of the drug during the course of treatment and proper disposal of unused drug. Contact local state professional licensing board or state-controlled substances authority for information on how to prevent and detect abuse or diversion of this product.

5.3 Life-Threatening Respiratory Depression

Serious, life-threatening, or fatal respiratory depression has been reported with the use of opioids, even when used as recommended. Respiratory depression, if not immediately recognized and treated, may lead to respiratory arrest and death. Management of respiratory depression may include close observation, supportive measures, and use of opioid antagonists, depending on the patient's clinical status [see Overdosage (10)] . Carbon dioxide (CO^2) retention from opioid-induced respiratory depression can exacerbate the sedating effects of opioids.

While serious, life-threatening, or fatal respiratory depression can occur at any time during the use of tramadol hydrochloride oral solution, the risk is greatest during the initiation of therapy or following a dosage increase.

To reduce the risk of respiratory depression, proper dosing and titration of tramadol hydrochloride oral solution are essential [see Dosage and Administration (2)] . Overestimating the tramadol hydrochloride oral solution dosage when converting patients from another opioid product can result in a fatal overdose with the first dose.
Accidental ingestion of even one dose of tramadol hydrochloride oral solution, especially by children, can result in respiratory depression and death due to an overdose of tramadol.

Educate patients and caregivers on how to recognize respiratory depression and emphasize the importance of calling 911 or getting emergency medical help right away in the event of a known or suspected overdose.

Opioids can cause sleep-related breathing disorders including central sleep apnea (CSA) and sleep-related hypoxemia. Opioid use increases the risk of CSA in a dose-dependent fashion. In patients who present with CSA, consider decreasing the opioid dosage using best practices for opioid taper [see Dosage and Administration (2.5)] .

Patient Access to Naloxone for the Emergency Treatment of Opioid Overdose

Discuss the availability of naloxone for the emergency treatment of opioid overdose with the patient and caregiver and assess the potential need for access to naloxone, both when initiating and renewing treatment with tramadol hydrochloride oral solution. Inform patients and caregivers about the various ways to obtain naloxone as permitted by individual state naloxone dispensing and prescribing requirements or guidelines (e.g., by prescription, directly from a pharmacist, or as part of a community-based program). Educate patients and caregivers on how to recognize respiratory depression and emphasize the importance of calling 911 or getting emergency medical help, even if naloxone is administered.

Consider prescribing naloxone, based on the patient’s risk factors for overdose, such as concomitant use of CNS depressants, a history of opioid use disorder, or prior opioid overdose. The presence of risk factors for overdose should not prevent the proper management of pain in any given patient. Also consider prescribing naloxone if the patient has household members (including children) or other close contacts at risk for accidental ingestion or overdose. If naloxone is prescribed, educate patients and caregivers on how to treat with naloxone [see Dosage and Administration (2.2), Warnings and Precautions (5.2, 5.3, 5.4), Overdosage (10)] .

5.4 Risks from Concomitant Use with Benzodiazepines or Other CNS Depressants

Profound sedation, respiratory depression, coma, and death may result from the concomitant use of tramadol hydrochloride oral solution with benzodiazepines and/or other CNS depressants , including alcohol (e.g., non-benzodiazepine sedatives/hypnotics, anxiolytics, tranquilizers, muscle relaxants, general anesthetics, antipsychotics, other opioids). Because of these risks, reserve concomitant prescribing of these drugs for use in patients for whom alternative treatment options are inadequate.

Observational studies have demonstrated that concomitant use of opioid analgesics and benzodiazepines increases the risk of drug-related mortality compared to use of opioid analgesics alone. Because of similar pharmacological properties, it is reasonable to expect similar risk with the concomitant use of other CNS depressant drugs with opioid analgesics [see Drug Interactions (7)] .

If the decision is made to prescribe a benzodiazepine or other CNS depressant concomitantly with an opioid analgesic, prescribe the lowest effective dosages and minimum durations of concomitant use. In patients already receiving an opioid analgesic, prescribe a lower initial dose of the benzodiazepine or other CNS depressant than indicated in the absence of an opioid, and titrate based on clinical response. If an opioid analgesic is initiated in a patient already taking a benzodiazepine or other CNS depressant, prescribe a lower initial dose of the opioid analgesic, and titrate based on clinical response. Inform patients and caregivers of this potential interaction and educate them on the signs and symptoms of respiratory depression (including sedation).

If concomitant use is warranted, consider prescribing naloxone for the emergency treatment of opioid overdose [see Dosage and Administration (2.2), Warnings and Precautions (5.3), Overdosage (10)] .

Advise both patients and caregivers about the risks of respiratory depression and sedation when tramadol hydrochloride oral solution is used with benzodiazepines or other CNS depressants (including alcohol and illicit drugs). Advise patients not to drive or operate heavy machinery until the effects of concomitant use of the benzodiazepine or other CNS depressant have been determined. Screen patients for risk of substance use disorders, including opioid abuse and misuse, and warn them of the risk for overdose and death associated with the use of additional CNS depressants including alcohol and illicit drugs [see Drug Interactions (7)] .

5.5 Neonatal Opioid Withdrawal Syndrome

Use of tramadol hydrochloride oral solution for an extended period of time during pregnancy can result in withdrawal in the neonate. Neonatal opioid withdrawal syndrome, unlike opioid withdrawal syndrome in adults, may be life-threatening if not recognized and treated, and requires management according to protocols developed by neonatology experts. Observe newborns for signs of neonatal opioid withdrawal syndrome and manage accordingly. Advise pregnant women using opioids for an extended period of time of the risk of neonatal opioid withdrawal syndrome and ensure that appropriate treatment will be available [see Use in Specific Populations (8.1)] .

5.6 Opioid Analgesic Risk Evaluation and Mitigation Strategy (REMS)

To ensure that the benefits of opioid analgesics outweigh the risks of addiction, abuse, and misuse, the Food and Drug Administration (FDA) has required a Risk Evaluation and Mitigation Strategy (REMS) for these products. Under the requirements of the REMS, drug companies with approved opioid analgesic products must make REMS-compliant education programs available to healthcare providers. Healthcare providers are strongly encouraged to do all of the following:

- Complete a REMS-compliant education program offered by an accredited provider of continuing education (CE) or another education program that includes all the elements of the FDA Education Blueprint for Health Care Providers Involved in the Management or Support of Patients with Pain.
- Discuss the safe use, serious risks, and proper storage and disposal of opioid analgesics with patients and/or their caregivers every time these medicines are prescribed. The Patient Counseling Guide (PCG) can be obtained at this link: www.fda.gov/OpioidAnalgesicREMSPCG.
- Emphasize to patients and their caregivers the importance of reading the Medication Guide that they will receive from their pharmacist every time an opioid analgesic is dispensed to them.
- Consider using other tools to improve patient, household, and community safety, such as patient-prescriber agreements that reinforce patient-prescriber responsibilities.

To obtain further information on the opioid analgesic REMS and for a list of accredited REMS CME/CE, call 1-800-503-0784, or log on to www.opioidanalgesicrems.com. FDA Blueprint can be found at www.fda.gov/OpioidAnalgesicREMSBlueprint.

5.7 Ultra-Rapid Metabolism of Tramadol and Other Risk Factors for Life-threatening Respiratory Depression in Children

Life-threatening respiratory depression and death have occurred in children who received tramadol. Tramadol and codeine are subject to variability in metabolism based upon CYP2D6 genotype (described below), which can lead to increased exposure to an active metabolite. Based upon postmarketing reports with tramadol or with codeine, children younger than 12 years of age may be more susceptible to the respiratory depressant effects of tramadol. Furthermore, children with obstructive sleep apnea who are treated with opioids for post-tonsillectomy and/or adenoidectomy pain may be particularly sensitive to their respiratory depressant effect. Because of the risk of life-threatening respiratory depression and death:

- Tramadol hydrochloride oral solution is contraindicated for all children younger than 12 years of age [see Contraindications (4)] .
- Tramadol hydrochloride oral solution is contraindicated for postoperative management in pediatric patients younger than 18 years of age following tonsillectomy and/or adenoidectomy [see Contraindications (4)] .
- Avoid the use of tramadol hydrochloride oral solution in adolescents 12 to 18 years of age who have other risk factors that may increase their sensitivity to the respiratory depressant effects of tramadol unless the benefits outweigh the risks. Risk factors include conditions associated with hypoventilation such as postoperative status, obstructive sleep apnea, obesity, severe pulmonary disease, neuromuscular disease, and concomitant use of other medications that cause respiratory depression.
- As with adults, when prescribing opioids for adolescents, healthcare providers should choose the lowest effective dose for the shortest period of time and inform patients and caregivers about these risks and the signs of opioid overdose [see Use in Specific Populations (8.4), Overdosage (10)] .

Nursing Mothers

Tramadol is subject to the same polymorphic metabolism as codeine, with ultra-rapid metabolizers of CYP2D6 substrates being potentially exposed to life-threatening levels of the active metabolite O-desmethyltramadol (M1). At least one death was reported in a nursing infant who was exposed to high levels of morphine in breast milk because the mother was an ultra-rapid metabolizer of codeine. A baby nursing from an ultra-rapid metabolizer mother taking tramadol hydrochloride oral solution could potentially be exposed to high levels of M1, and experience life-threatening respiratory depression. For this reason, breastfeeding is not recommended during treatment with tramadol hydrochloride oral solution [see Use in Specific Populations (8.2)] .

CYP2D6 Genetic Variability: Ultra-rapid Metabolizer

Some individuals may be ultra-rapid metabolizers because of a specific CYP2D6 genotype (e.g., gene duplications denoted as *1/*1×N or *1/*2×N). The prevalence of this CYP2D6 phenotype varies widely and has been estimated at 1 to 10% for Whites (European, North American), 3 to 4% for Blacks (African Americans), 1 to 2% for East Asians (Chinese, Japanese, Korean), and may be greater than 10% in certain racial/ethnic groups (i.e., Oceanian, Northern African, Middle Eastern, Ashkenazi Jews, Puerto Rican). These individuals convert tramadol into its active metabolite, O-desmethyltramadol (M1), more rapidly and completely than other people. This rapid conversion results in higher than expected serum M1 levels. Even at labeled dosage regimens, individuals who are ultra-rapid metabolizers may have life-threatening or fatal respiratory depression or experience signs of overdose (such as extreme sleepiness, confusion, or shallow breathing) [see Overdosage (10)] . Therefore, individuals who are ultra-rapid metabolizers should not use tramadol hydrochloride oral solution.

5.8 Risks of Interactions with Drugs Affecting Cytochrome P450 Isoenzymes

The effects of concomitant use or discontinuation of cytochrome P450 3A4 inducers, 3A4 inhibitors, or 2D6 inhibitors on levels of tramadol and M1 from tramadol hydrochloride oral solution are complex. Use of cytochrome P450 3A4 inducers, 3A4 inhibitors, or 2D6 inhibitors with tramadol hydrochloride oral solution requires careful consideration of the effects on the parent drug, tramadol which is a weak serotonin and norepinephrine reuptake inhibitor and μ-opioid agonist, and the active metabolite, M1, which is more potent than tramadol in μ-opioid receptor binding [see Drug Interactions (7)] .

Risks of Concomitant Use or Discontinuation of Cytochrome P450 2D6 Inhibitors

The concomitant use of tramadol hydrochloride oral solution with all cytochrome P450 2D6 inhibitors (e.g., amiodarone, quinidine) may result in an increase in tramadol plasma levels and a decrease in the levels of the active metabolite, M1. A decrease in M1 exposure in patients who have developed physical dependence to tramadol, may result in signs and symptoms of opioid withdrawal and reduced efficacy. The effect of increased tramadol levels may be an increased risk for serious adverse events including seizures and serotonin syndrome.

Discontinuation of a concomitantly used cytochrome P450 2D6 inhibitor may result in a decrease in tramadol plasma levels and an increase in active metabolite M1 levels, which could increase or prolong adverse reactions related to opioid toxicity and may cause potentially fatal respiratory depression.

Evaluate patients receiving tramadol hydrochloride oral solution and any CYP2D6 inhibitor at frequent intervals for the risk of serious adverse events including seizures and serotonin syndrome, signs and symptoms that may reflect opioid toxicity, and opioid withdrawal when tramadol hydrochloride oral solution is used in conjunction with inhibitors of CYP2D6 [see Drug Interactions (7)] .

Cytochrome P450 3A4 Interaction

The concomitant use of tramadol hydrochloride oral solution with cytochrome P450 3A4 inhibitors, such as macrolide antibiotics (e.g., erythromycin), azole-antifungal agents (e.g., ketoconazole), and protease inhibitors (e.g., ritonavir) or discontinuation of a cytochrome P450 3A4 inducer such as rifampin, carbamazepine, and phenytoin, may result in an increase in tramadol plasma concentrations, which could increase or prolong adverse reactions, increase the risk for serious adverse events including seizures and serotonin syndrome, and may cause potentially fatal respiratory depression.

The concomitant use of tramadol hydrochloride oral solution with all cytochrome P450 3A4 inducers or discontinuation of a cytochrome P450 3A4 inhibitor may result in lower tramadol levels. This may be associated with a decrease in efficacy, and in some patients, may result in signs and symptoms of opioid withdrawal.

Evaluate patients receiving tramadol hydrochloride oral solution and any CYP3A4 inhibitor or inducer at frequent intervals for the risk for serious adverse events including seizures and serotonin syndrome, signs and symptoms that may reflect opioid toxicity and opioid withdrawal when tramadol hydrochloride oral solution is used in conjunction with inhibitors and inducers of CYP3A4 [see Drug Interactions (7)] .

5.9 Opioid-Induced Hyperalgesia and Allodynia

Opioid-Induced Hyperalgesia and Allodynia Opioid-Induced Hyperalgesia (OIH) occurs when an opioid analgesic paradoxically causes an increase in pain, or an increase in sensitivity to pain. This condition differs from tolerance, which is the need for increasing doses of opioids to maintain a defined effect [see Dependence (9.3)] . Symptoms of OIH include (but may not be limited to) increased levels of pain upon opioid dosage increase, decreased levels of pain upon opioid dosage decrease, or pain from ordinarily non-painful stimuli (allodynia). These symptoms may suggest OIH only if there is no evidence of underlying disease progression, opioid tolerance, opioid withdrawal, or addictive behavior.

Cases of OIH have been reported, both with short-term and longer-term use of opioid analgesics. Though the mechanism of OIH is not fully understood, multiple biochemical pathways have been implicated. Medical literature suggests a strong biologic plausibility between opioid analgesics and OIH and allodynia. If a patient is suspected to be experiencing OIH, carefully consider appropriately decreasing the dose of the current opioid analgesic or opioid rotation (safely switching the patient to a different opioid moiety) [see Dosage and Administration (2.5), Warnings and Precautions (5.19)]

5.10 Serotonin Syndrome Risk

Cases of serotonin syndrome, a potentially life-threatening condition, have been reported with the use of tramadol products, including tramadol hydrochloride oral solution, particularly during concomitant use with serotonergic drugs. Serotonergic drugs include selective serotonin reuptake inhibitors (SSRIs), serotonin and norepinephrine reuptake inhibitors (SNRIs), tricyclic antidepressants (TCAs), triptans, 5-HT3 receptor antagonists, drugs that affect the serotonergic neurotransmitter system (e.g., mirtazapine, trazodone, tramadol), certain muscle relaxants (i.e., cyclobenzaprine, metaxalone), and drugs that impair metabolism of serotonin (including monoamine oxidase inhibitors, both those intended to treat psychiatric disorders and also others, such as linezolid and intravenous methylene blue) [see Drug Interactions (7)] . This may occur within the recommended dosage range.

Serotonin syndrome symptoms may include mental status changes (e.g., agitation, hallucinations, coma), autonomic instability (e.g., tachycardia, labile blood pressure, hyperthermia), neuromuscular aberrations (e.g., hyperreflexia, incoordination, rigidity), and/or gastrointestinal symptoms (e.g., nausea, vomiting, diarrhea) and can be fatal. The onset of symptoms generally occurs within several hours to a few days of concomitant use but may occur later than that. Discontinue tramadol hydrochloride oral solution if serotonin syndrome is suspected.

5.11 Increased Risk of Seizures

Seizures have been reported in patients receiving tramadol hydrochloride oral solution within the recommended dosage range. Spontaneous postmarketing reports indicate that seizure risk is increased with doses of tramadol hydrochloride oral solution above the recommended range.

Concomitant use of tramadol hydrochloride oral solution increases the seizure risk in patients taking [see Drug Interactions (7)] :

- Selective serotonin re-uptake inhibitors (SSRI antidepressants or anorectics),
- Tricyclic antidepressants (TCAs), and other tricyclic compounds (e.g., cyclobenzaprine, promethazine, etc.),
- Other opioids,
- Monoamine oxidase inhibitors (MAOI) [see Warnings and Precautions (5.10), Drug Interactions (7)] .
- Neuroleptics, or
- Other drugs that reduce the seizure threshold.

Risk of seizure may also increase in patients with epilepsy, those with a history of seizures, or in patients with a recognized risk for seizure (such as head trauma, metabolic disorders, alcohol and drug withdrawal, CNS infections). In tramadol hydrochloride oral solution overdose, naloxone administration may increase the risk of seizure [see Overdosage (10)] .

5.12 Suicide Risk

- Do not prescribe tramadol hydrochloride oral solution for patients who are suicidal or addiction-prone. Consideration should be given to the use of non-narcotic analgesics in patients who are suicidal or depressed [see Drug Abuse and Dependence (9.2)] .
- Prescribe tramadol hydrochloride oral solution with caution for patients with a history of misuse and/or are currently taking CNS-active drugs including tranquilizers or antidepressant drugs, alcohol in excess, and patients who suffer from emotional disturbance or depression [see Drug Interactions (7)] .
- Inform patients not to exceed the recommended dose and to limit their intake of alcohol [see Dosage and Administration (2.1), Warnings and Precautions (5.4)] .

5.13 Life-Threatening Respiratory Depression in Patients with Chronic Pulmonary Disease or in Elderly, Cachectic, or Debilitated Patients

The use of tramadol hydrochloride oral solution in patients with acute or severe bronchial asthma in an unmonitored setting or in the absence of resuscitative equipment is contraindicated.

Patients with Chronic Pulmonary Disease

Tramadol hydrochloride oral solution-treated patients with significant chronic obstructive pulmonary disease or cor pulmonale, and those with a substantially decreased respiratory reserve, hypoxia, hypercapnia, or pre-existing respiratory depression are at increased risk of decreased respiratory drive including apnea, even at recommended dosages of tramadol hydrochloride oral solution [see Warnings and Precautions (5.3)] .

Elderly, Cachectic, or Debilitated Patients

Life-threatening respiratory depression is more likely to occur in elderly, cachectic, or debilitated patients because they may have altered pharmacokinetics or altered clearance compared to younger, healthier patients [see Warnings and Precautions (5.3)] .

Regularly evaluate patients closely, particularly when initiating and titrating tramadol hydrochloride oral solution and when tramadol hydrochloride oral solution is given concomitantly with other drugs that depress respiration [see Warnings and Precautions (5.3, 5.4), Drug Interactions (7)] . Alternatively, consider the use of non-opioid analgesics in these patients.

5.14 Adrenal Insufficiency

Cases of adrenal insufficiency have been reported with opioid use, more often following greater than one month of use. Presentation of adrenal insufficiency may include non-specific symptoms and signs including nausea, vomiting, anorexia, fatigue, weakness, dizziness, and low blood pressure. If adrenal insufficiency is suspected, confirm the diagnosis with diagnostic testing as soon as possible. If adrenal insufficiency is diagnosed, treat with physiologic replacement doses of corticosteroids. Wean the patient off of the opioid to allow adrenal function to recover and continue corticosteroid treatment until adrenal function recovers. Other opioids may be tried as some cases reported use of a different opioid without recurrence of adrenal insufficiency. The information available does not identify any particular opioids as being more likely to be associated with adrenal insufficiency.

5.15 Severe Hypotension

Tramadol hydrochloride oral solution may cause severe hypotension including orthostatic hypotension and syncope in ambulatory patients. There is increased risk in patients whose ability to maintain blood pressure has already been compromised by a reduced blood volume or concurrent administration of certain CNS depressant drugs (e.g. phenothiazines or general anesthetics) [see Drug Interactions (7)] . Regularly evaluate patients for signs of hypotension after initiating or titrating the dosage of tramadol hydrochloride oral solution. In patients with circulatory shock, tramadol hydrochloride oral solution may cause vasodilation that can further reduce cardiac output and blood pressure. Avoid the use of tramadol hydrochloride oral solution in patients with circulatory shock.

5.16 Risks of use in Patients with Increased Intracranial Pressure, Brain Tumors, Head Injury, or Impaired Consciousness

In patients who may be susceptible to the intracranial effects of CO2retention (e.g., those with evidence of increased intracranial pressure or brain tumors), tramadol hydrochloride oral solution may reduce respiratory drive, and the resultant CO2retention can further increase intracranial pressure. Monitor such patients for signs of sedation and respiratory depression, particularly when initiating therapy with tramadol hydrochloride oral solution.

Opioids may also obscure the clinical course in a patient with a head injury. Avoid the use of tramadol hydrochloride oral solution in patients with impaired consciousness or coma.

5.17 Risks of Use in Patients with Gastrointestinal Conditions

Tramadol hydrochloride oral solution is contraindicated in patients with known or suspected gastrointestinal obstruction, including paralytic ileus [see Contraindications (4)] .

The tramadol in tramadol hydrochloride oral solution may cause spasm of the sphincter of Oddi. Opioids may cause increases in serum amylase. Regularly evaluate patients with biliary tract disease, including acute pancreatitis for worsening symptoms.

5.18 Anaphylaxis and Other Hypersensitivity Reactions

Serious and rarely fatal anaphylactic reactions have been reported in patients receiving therapy with tramadol hydrochloride oral solution. When these events do occur, it is often following the first dose. Other reported allergic reactions include pruritus, hives, bronchospasm, angioedema, toxic epidermal necrolysis and Stevens-Johnson syndrome. Patients with a history of hypersensitivity reactions to tramadol and other opioids may be at increased risk and therefore should not receive tramadol hydrochloride oral solution [see Contraindications (4)] . If anaphylaxis or other hypersensitivity occurs, stop administration of tramadol hydrochloride oral solution immediately, discontinue tramadol hydrochloride oral solution permanently, and do not rechallenge with any formulation of tramadol. Advise patients to seek immediate medical attention if they experience any symptoms of a hypersensitivity reaction. [see Contraindications (4)] .

5.19 Withdrawal

Do not abruptly discontinue tramadol hydrochloride oral solution in a patient physically dependent on opioids. When discontinuing tramadol hydrochloride oral solution in a physically dependent patient, gradually taper the dosage. Rapid tapering of tramadol in a patient physically dependent on opioids may lead to a withdrawal syndrome and return of pain [see Dosage and Administration (2.5), Drug Abuse and Dependence (9.3)] .

Additionally, avoid the use of mixed agonist/antagonist (e.g., pentazocine, nalbuphine, and butorphanol) or partial agonist (e.g., buprenorphine) analgesics in patients who are receiving a full opioid agonist analgesic, including tramadol hydrochloride oral solution. In these patients, mixed agonist/antagonist and partial agonist analgesics may reduce the analgesic effect and/or precipitate withdrawal symptoms [see Drug Interactions (7)] .

5.20 Driving and Operating Machinery

tramadol hydrochloride oral solution may impair the mental or physical abilities needed to perform potentially hazardous activities such as driving a car or operating machinery. Warn patients not to drive or operate dangerous machinery unless they are tolerant to the effects of tramadol hydrochloride oral solution and know how they will react to the medication.

5.21 Hyponatremia

Hyponatremia (serum sodium < 135 mmol/L) has been reported with the use of tramadol, and many cases are severe (sodium level < 120 mmol/L). Most cases of hyponatremia occurred in females over the age of 65 and within the first week of therapy. In some reports, hyponatremia resulted from the syndrome of inappropriate antidiuretic hormone secretion (SIADH). Monitor for signs and symptoms of hyponatremia (e.g., confusion, disorientation), during treatment with tramadol hydrochloride oral solution, especially during initiation of therapy. If signs and symptoms of hyponatremia are present, initiate appropriate treatment (e.g., fluid restriction) and discontinue tramadol hydrochloride oral solution [see Dosage and Administration(2.5)] .

5.22 Hypoglycemia

Cases of tramadol-associated hypoglycemia have been reported, some resulting in hospitalization. In most cases, patients had predisposing risk factors (e.g. diabetes). If hypoglycemia is suspected, monitor blood glucose levels and consider drug discontinuation as appropriate [see Dosage and Administration(2.5)] .

6 ADVERSE REACTIONS

The following serious adverse reactions are described, or described in greater detail, in other sections:

- Addiction, Abuse, and Misuse [see Warnings and Precautions (5.2) ]
- Life-Threatening Respiratory Depression [see Warnings and Precautions (5.3)]
- Interactions with Benzodiazepines or Other CNS Depressants [see Warnings and Precautions (5.4)]
- Neonatal Opioid Withdrawal Syndrome [see Warnings and Precautions (5.5)]
- Ultra-Rapid Metabolism of Tramadol and Other Risk Factors for Life-threatening Respiratory Depression in Children [see Warnings and Precautions (5.7)]
- Opioid-Induced Hyperalgesia and Allodynia [see Warnings and Precautions (5.9)]
- Serotonin Syndrome [see Warnings and Precautions (5.10)]
- Seizures [see Warnings and Precautions (5.11)]
- Suicide [see Warnings and Precautions (5.12)]
- Adrenal Insufficiency [see Warnings and Precautions (5.14)]
- Severe Hypotension [see Warnings and Precautions (5.15)]
- Gastrointestinal Adverse Reactions [see Warnings and Precautions (5.17)]
- Hypersensitivity Reactions [see Warnings and Precautions (5.18)]
- Withdrawal [see Warnings and Precautions (5.19)]

6.1 Clinical Trials Experience

Because clinical trials are conducted under widely varying conditions, adverse reaction rates observed in the clinical trials of a drug cannot be directly compared to rates in the clinical trials of another drug and may not reflect the rates observed in practice.

Tramadol hydrochloride was administered to 550 patients during the double-blind or open-label extension periods in U.S. studies of chronic nonmalignant pain. Of these patients, 375 were 65 years old or older. Table 1 reports the cumulative incidence rate of adverse reactions by 7, 30 and 90 days for the most frequent reactions (5% or more by 7 days). The most frequently reported events were in the central nervous system and gastrointestinal system. Although the reactions listed in the table are felt to be probably related to tramadol hydrochloride administration, the reported rates also include some events that may have been due to underlying disease or concomitant medication. The overall incidence rates of adverse experiences in these trials were similar for tramadol hydrochloride and the active control groups, TYLENOL with Codeine #3 (acetaminophen 300 mg with codeine phosphate 30 mg), and aspirin 325 mg with codeine phosphate 30 mg, however, the rates of withdrawals due to adverse events appeared to be higher in the tramadol hydrochloride groups.

Table 1: Cumulative Incidence of Adverse Reactions for Tramadol HCl Tablets in Chronic Trials of Nonmalignant Pain (N=427)
 | Up to 7 Days | Up to 30 Days | Up to 90 Days
Dizziness/Vertigo | 26% | 31% | 33%
Nausea | 24% | 34% | 40%
Constipation | 24% | 38% | 46%
Headache | 18% | 26% | 32%
Somnolence | 16% | 23% | 25%
Vomiting | 9% | 13% | 17%
Pruritus | 8% | 10% | 11%
CNS Stimulation [CNS Stimulation is a composite of nervousness, anxiety, agitation, tremor, spasticity, euphoria, emotional lability and hallucinations] | 7% | 11% | 14%
Asthenia | 6% | 11% | 12%
Sweating | 6% | 7% | 9%
Dyspepsia | 5% | 9% | 13%
Dry Mouth | 5% | 9% | 10%
Diarrhea | 5% | 6% | 10%

Incidence 1% to Less than 5% Possibly Causally Related

The following lists adverse reactions that occurred with an incidence of 1% to less than 5% in clinical trials, and for which the possibility of a causal relationship with tramadol hydrochloride exists.

Body as a Whole: Malaise.

Cardiovascular: Vasodilation.

Central Nervous System: Anxiety, Confusion, Coordination disturbance, Euphoria, Miosis, Nervousness, Sleep disorder.

Gastrointestinal: Abdominal pain, Anorexia, Flatulence.

Musculoskeletal: Hypertonia.

Skin: Rash.

Special Senses: Visual disturbance.

Urogenital: Menopausal symptoms, Urinary frequency, Urinary retention.

Incidence Less than 1%, Possibly Causally Related

The following lists adverse reactions that occurred with an incidence of less than 1% in clinical trials of tramadol and/or reported in postmarketing experience with tramadol-containing products.

Body as a Whole: Accidental injury, Allergic reaction, Anaphylaxis, Death, Suicidal tendency, Weight loss, Serotonin syndrome (mental status change, hyperreflexia, fever, shivering, tremor, agitation, diaphoresis, seizures and coma).

Cardiovascular: Orthostatic hypotension, Syncope, Tachycardia.

Central Nervous System: Abnormal gait, Amnesia, Cognitive dysfunction, Depression, Difficulty in concentration, Hallucinations, Paresthesia, Seizure, Tremor.

Respiratory: Dyspnea.

Skin: Stevens-Johnson syndrome/Toxic epidermal necrolysis, Urticaria, Vesicles.

Special Senses: Dysgeusia.

Urogenital: Dysuria, Menstrual disorder.

Other Adverse Experiences, Causal Relationship Unknown

A variety of other adverse events were reported infrequently in patients taking tramadol hydrochloride during clinical trials and/or reported in postmarketing experience. A causal relationship between tramadol hydrochloride and these events has not been determined. However, the most significant events are listed below as alerting information to the physician.

Cardiovascular: Abnormal ECG, Hypertension, Hypotension, Myocardial ischemia, Palpitations, Pulmonary edema, Pulmonary embolism.

Central Nervous System: Migraine.

Gastrointestinal: Gastrointestinal bleeding, Hepatitis, Stomatitis, Liver failure.

Laboratory Abnormalities: Creatinine increase, Elevated liver enzymes, Hemoglobin decrease, Proteinuria.

Sensory: Cataracts, Deafness, Tinnitus.

6.2 Postmarketing Experience

The following adverse reactions have been identified during post-approval use of tramadol hydrochloride. Because these reactions are reported voluntarily from a population of uncertain size, it is not always possible to reliably estimate their frequency or establish a causal relationship to drug exposure.

Serotonin syndrome: Cases of serotonin syndrome, a potentially life-threatening condition, have been reported during concomitant use of opioids with serotonergic drugs.

Adrenal insufficiency: Cases of adrenal insufficiency have been reported with opioid use, more often following greater than one month of use.

Androgen deficiency: Cases of androgen deficiency have occurred with use of opioids for an extended period of time. [see Clinical Pharmacology (12.2)] .

QT prolongation/torsade de pointes: Cases of QT prolongation and/or torsade de pointeshave been reported with tramadol use. Many of these cases were reported in patients taking another drug labeled for QT prolongation, in patients with a risk factor for QT prolongation (e.g., hypokalemia), or in the overdose setting.

Eye disorders– mydriasis

Metabolism and nutrition disorders

Hyponatremia: Cases of severe hyponatremia and/or SIADH have been reported in patients taking tramadol, most often in females over the age of 65, and within the first week of therapy [see Warnings and Precautions (5.21)] .

Hypoglycemia: Cases of hypoglycemia have been reported in patients taking tramadol. Most reports were in patients with predisposing risk factors, including diabetes or renal insufficiency, or in elderly patients [see Warnings and Precautions (5.22)] .

Nervous system disorders– movement disorder, speech disorder

Psychiatric disorders– delirium

Hyperalgesia and Allodynia: Cases of hyperalgesia and allodynia have been reported with opioid therapy of any duration [see Warnings and Precautions (5.9)] .

7 DRUG INTERACTIONS

Table 2: Clinically Significant Drug Interactions with Tramadol Hydrochloride Oral Solution
Inhibitors of CYP2D6
Clinical Impact: | The concomitant use of tramadol hydrochloride oral solution and CYP2D6 inhibitors may result in an increase in the plasma concentration of tramadol and a decrease in the plasma concentration of M1, particularly when an inhibitor is added after a stable dose of tramadol hydrochloride oral solution is achieved. Since M1 is a more potent µ-opioid agonist, decreased M1 exposure could result in decreased therapeutic effects, and may result in signs and symptoms of opioid withdrawal in patients who had developed physical dependence to tramadol. Increased tramadol exposure can result in increased or prolonged therapeutic effects and increased risk for serious adverse events including seizures and serotonin syndrome. After stopping a CYP2D6 inhibitor, as the effects of the inhibitor decline, the tramadol plasma concentration will decrease and the M1 plasma concentration will increase. This could increase or prolong therapeutic effects but also increase adverse reactions related to opioid toxicity, such as potentially fatal respiratory depression [see Clinical Pharmacology (12.3)] .
Intervention: | If concomitant use of a CYP2D6 inhibitor is necessary, evaluate patients at frequent intervals for adverse reactions including opioid withdrawal, seizures and serotonin syndrome. If a CYP2D6 inhibitor is discontinued, consider lowering tramadol hydrochloride oral solution dosage until stable drug effects are achieved. Evaluate patients at frequent intervals for adverse events including respiratory depression and sedation.
Examples | Quinidine, fluoxetine, paroxetine and bupropion
Inhibitors of CYP3A4
Clinical Impact: | The concomitant use of tramadol hydrochloride oral solution and CYP3A4 inhibitors can increase the plasma concentration of tramadol and may result in a greater amount of metabolism via CYP2D6 and greater levels of M1. Evaluate patients closely for increased risk of serious adverse events including seizures and serotonin syndrome, and adverse reactions related to opioid toxicity including potentially fatal respiratory depression, particularly when an inhibitor is added after a stable dose of tramadol hydrochloride oral solution is achieved. After stopping a CYP3A4 inhibitor, as the effects of the inhibitor decline, the tramadol plasma concentration will decrease [see Clinical Pharmacology (12.3)] , resulting in decreased opioid efficacy or a withdrawal syndrome in patients who had developed physical dependence to tramadol.
Intervention: | If concomitant use is necessary, consider dosage reduction of tramadol hydrochloride oral solution until stable drug effects are achieved. Inform patients and caregivers of this potential interaction and educate them on the signs and symptoms of seizures, serotonin syndrome, and signs of respiratory depression and sedation at frequent intervals. If a CYP3A4 inhibitor is discontinued, consider increasing the tramadol hydrochloride oral solution dosage until stable drug effects are achieved and evaluate patients at frequent intervals for signs and symptoms of opioid withdrawal.
Examples | Macrolide antibiotics (e.g., erythromycin), azole-antifungal agents (e.g. ketoconazole), protease inhibitors (e.g., ritonavir)
CYP3A4 Inducers
Clinical Impact: | The concomitant use of tramadol hydrochloride oral solution and CYP3A4 inducers can decrease the plasma concentration of tramadol [see Clinical Pharmacology (12.3)] , resulting in decreased efficacy or onset of a withdrawal syndrome in patients who have developed physical dependence to tramadol [see Warnings and Precautions (5.8)] . After stopping a CYP3A4 inducer, as the effects of the inducer decline, the tramadol plasma concentration will increase [see Clinical Pharmacology (12.3)] , which could increase or prolong both the therapeutic effects and adverse reactions, and may cause seizures, serotonin syndrome, and/or potentially fatal respiratory depression.
Intervention: | If concomitant use is necessary, consider increasing the tramadol hydrochloride oral solution dosage until stable drug effects are achieved. Evaluate patients for signs of opioid withdrawal. If a CYP3A4 inducer is discontinued, consider tramadol hydrochloride oral solution dosage reduction and evaluate patients at frequent intervals for seizures and serotonin syndrome, and signs of respiratory depression and sedation. Patients taking carbamazepine, a CYP3A4 inducer, may have a significantly reduced analgesic effect of tramadol. Because carbamazepine increases tramadol metabolism and because of the seizure risk associated with tramadol, concomitant administration of tramadol hydrochloride oral solution and carbamazepine is not recommended.
Examples | Rifampin, carbamazepine, phenytoin
Benzodiazepines and Other Central Nervous System (CNS) Depressants
Clinical Impact: | Due to additive pharmacologic effect, the concomitant use of benzodiazepines or other CNS depressants, including alcohol, increases the risk of respiratory depression, profound sedation, coma, and death [see Warnings and Precautions (5.4)] .
Intervention: | Reserve concomitant prescribing of these drugs for use in patients for whom alternative treatment options are inadequate. Limit dosages and durations to the minimum required. Inform patients and caregivers of this potential interaction and educate them on the signs and symptoms of respiratory depression (including sedation). If concomitant use is warranted, consider prescribing naloxone for the emergency treatment of opioid overdose [see Dosage and Administration (2.2), Warnings and Precautions (5.2, 5.3, 5.4)] .
Examples | Benzodiazepines and other sedatives/hypnotics, anxiolytics, tranquilizers, muscle relaxants, general anesthetics, antipsychotics, other opioids, and alcohol.
Serotonergic Drugs
Clinical Impact: | The concomitant use of opioids with other drugs that affect the serotonergic neurotransmitter system has resulted in serotonin syndrome [see Warnings and Precautions (5.10)] .
Intervention: | If concomitant use is warranted, frequently evaluate the patient, particularly during treatment initiation and dose adjustment. Discontinue tramadol hydrochloride oral solution immediately if serotonin syndrome is suspected.
Examples | Selective serotonin reuptake inhibitors (SSRIs), serotonin and norepinephrine reuptake inhibitors (SNRIs), tricyclic antidepressants (TCAs), triptans, 5-HT3 receptor antagonists, drugs that affect the serotonin neurotransmitter system (e.g., mirtazapine, trazodone, tramadol), certain muscle relaxants (i.e., cyclobenzaprine, metaxalone), monoamine oxidase inhibitors (those intended to treat psychiatric disorders and also others, such as linezolid and intravenous methylene blue).
Monoamine Oxidase Inhibitors (MAOIs)
Clinical Impact: | MAOI interactions with opioids may manifest as serotonin syndrome [see Warnings and Precautions (5.10)] or opioid toxicity (e.g., respiratory depression, coma) [see Warnings and Precautions (5.3)] .
Intervention: | Do not use tramadol hydrochloride oral solution in patients taking MAOIs or within 14 days of stopping such treatment.
Examples | phenelzine, tranylcypromine, linezolid
Mixed Agonist/Antagonist and Partial Agonist Opioid Analgesics
Clinical Impact: | May reduce the analgesic effect of tramadol hydrochloride oral solution and/or precipitate withdrawal symptoms.
Intervention: | Avoid concomitant use.
Examples | butorphanol, nalbuphine, pentazocine, buprenorphine
Muscle Relaxants
Clinical Impact: | Tramadol may enhance the neuromuscular blocking action of skeletal muscle relaxants and produce an increased degree of respiratory depression.
Intervention: | Because respiratory depression may be greater than otherwise expected, decrease the dosage of tramadol hydrochloride oral solution and/or the muscle relaxant as necessary. Due to the risk of respiratory depression with concomitant use of skeletal muscle relaxants and opioids, consider prescribing naloxone for the emergency treatment of opioid overdose [see Dosage and Administration (2.2), Warnings and Precautions (5.3, 5.4)] .
Diuretics
Clinical Impact: | Opioids can reduce the efficacy of diuretics by inducing the release of antidiuretic hormone.
Intervention: | Evaluate patients for signs of diminished diuresis and/or effects on blood pressure and increase the dosage of the diuretic as needed.
Anticholinergic Drugs
Clinical Impact: | The concomitant use of anticholinergic drugs may increase risk of urinary retention and/or severe constipation, which may lead to paralytic ileus.
Intervention: | Evaluate patients for signs of urinary retention or reduced gastric motility when tramadol hydrochloride oral solution is used concomitantly with anticholinergic drugs.
Digoxin
Clinical Impact: | Postmarketing surveillance of tramadol has revealed rare reports of digoxin toxicity.
Intervention: | Evaluate patients at frequent intervals for signs of digoxin toxicity and adjust dosage of digoxin as needed.
Warfarin
Clinical Impact: | Postmarketing surveillance of tramadol has revealed rare reports of alteration of warfarin effect, including elevation of prothrombin times.
Intervention: | Frequently reevaluate the prothrombin time of patients on warfarin for signs of an interaction and adjust the dosage of warfarin as needed.

8 USE IN SPECIFIC POPULATIONS

8.1 Pregnancy

Risk Summary

Use of opioid analgesics for an extended period of time during pregnancy may cause neonatal opioid withdrawal syndrome [see Warnings and Precautions (5.5)] . Available data with tramadol hydrochloride oral solution in pregnant women are insufficient to inform a drug-associated risk for major birth defects and miscarriage or adverse maternal outcomes. There are adverse outcomes reported with fetal exposure to opioid analgesics (see Clinical Considerations).

In animal reproduction studies, tramadol administration during organogenesis decreased fetal weights and reduced ossification in mice, rats, and rabbits at 1.4, 0.6, and 3.6 times the maximum recommended human daily dosage (MRHD). In a pre- and post-natal development study, tramadol decreased pup body weight and increased pup mortality at 1.2 and 1.9 times the MRHD. In a published study, tramadol caused structural abnormalities in the brains of fetuses when administered to female Sprague Dawley rats from Gestation Days 10-21 at a dose comparable to the MRHD [see Data] . Based on animal data, advise pregnant women of the potential risk to a fetus.

The background risk of major birth defects and miscarriage for the indicated population is unknown. All pregnancies have a background risk of birth defect, loss, or other adverse outcomes. In the U.S. general population, the estimated background risk of major birth defects and miscarriage in clinically recognized pregnancies is 2 to 4% and 15 to 20%, respectively.

Clinical Considerations

Fetal/Neonatal Adverse Reactions

Use of opioid analgesics for an extended period of time during pregnancy for medical or nonmedical purposes can result in respiratory depression and physical dependence in the neonate and neonatal opioid withdrawal syndrome shortly after birth.

Neonatal opioid withdrawal syndrome can present as irritability, hyperactivity and abnormal sleep pattern, high pitched cry, tremor, vomiting, diarrhea and failure to gain weight. The onset, duration, and severity of neonatal opioid withdrawal syndrome vary based on the specific opioid used, duration of use, timing and amount of last maternal use, and rate of elimination of the drug by the newborn. Observe newborns for symptoms and signs of neonatal opioid withdrawal syndrome and manage accordingly [see Warnings and Precautions (5.5)] .

Neonatal seizures, neonatal withdrawal syndrome, fetal death and still birth have been reported during postmarketing.

Labor or Delivery

Opioids cross the placenta and may produce respiratory depression and psycho-physiologic effects in neonates. An opioid antagonist, such as naloxone, must be available for reversal of opioid-induced respiratory depression in the neonate. Tramadol hydrochloride oral solution is not recommended for use in pregnant women during or immediately prior to labor, when other analgesic techniques are more appropriate. Opioid analgesics, including tramadol hydrochloride oral solution, can prolong labor through actions which temporarily reduce the strength, duration, and frequency of uterine contractions. However, this effect is not consistent and may be offset by an increased rate of cervical dilation, which tends to shorten labor. Monitor neonates exposed to opioid analgesics during labor for signs of excess sedation and respiratory depression.

Tramadol has been shown to cross the placenta. The mean ratio of serum tramadol in the umbilical veins compared to maternal veins was 0.83 for 40 women given tramadol during labor.

The effect of tramadol hydrochloride, if any, on the later growth, development, and functional maturation of the child is unknown.

Data

Animal Data

Tramadol has been shown to be embryotoxic and fetotoxic in mice, (120 mg/kg), rats (25 mg/kg) and rabbits (75 mg/kg) at maternally toxic dosages, but did not cause malformations at these dose levels. These doses on a mg/m^2basis are 1.4, 0.6, and 3.6 times the maximum recommended human daily dosage (MRHD) for mouse, rat and rabbit, respectively.

No drug-related malformations were observed in progeny of mice (up to 140 mg/kg), rats (up to 80 mg/kg) or rabbits (up to 300 mg/kg) treated with tramadol by various routes. Embryo and fetal toxicity consisted primarily of decreased fetal weights, decreased skeletal ossification and increased supernumerary ribs at maternally toxic dose levels. Transient delays in developmental or behavioral parameters were also seen in pups from rat dams allowed to deliver. Embryo and fetal lethality were reported only in one rabbit study at 300 mg/kg, a dose that would cause extreme maternal toxicity in the rabbit. The dosages listed for mouse, rat and rabbit are 1.7, 1.9 and 14.6 times the MRHD, respectively.

Tramadol was evaluated in pre- and post-natal studies in rats. Progeny of dams receiving oral (gavage) dose levels of 50 mg/kg (1.2 times the MRHD) or greater had decreased weights, and pup survival was decreased early in lactation at 80 mg/kg (1.9 times the MRHD).

8.2 Lactation

Risk Summary

Tramadol hydrochloride oral solution is not recommended for obstetrical preoperative medication or for post-delivery analgesia in nursing mothers because its safety in infants and newborns has not been well studied.

Tramadol and its metabolite, O-desmethyltramadol (M1), are present in human milk. There is no information on the effects of the drug on the breastfed infant or the effects of the drug on milk production. The M1 metabolite is more potent than tramadol in mu opioid receptor binding [see Clinical Pharmacology (12)] . Published studies have reported tramadol and M1 in colostrum with administration of tramadol to nursing mothers in the early post-partum period. Women who are ultra-rapid metabolizers of tramadol may have higher than expected serum levels of M1, potentially leading to higher levels of M1 in breast milk that can be dangerous in their breastfed infants. In women with normal tramadol metabolism, the amount of tramadol secreted into human milk is low and dose-dependent. Because of the potential for serious adverse reactions, including excess sedation and respiratory depression in a breastfed infant, advise patients that breastfeeding is not recommended during treatment with tramadol hydrochloride oral solution [see Warnings and Precautions (5.3, 5.5)] .

Clinical Considerations

If infants are exposed to tramadol hydrochloride oral solution through breast milk, they should be monitored for excess sedation and respiratory depression. Withdrawal symptoms can occur in breastfed infants when maternal administration of an opioid analgesic is stopped, or when breast-feeding is stopped.

Data

Following a single IV 100 mg dose of tramadol, the cumulative excretion in breast milk within 16 hours post dose was 100 mcg of tramadol (0.1% of the maternal dose) and 27 mcg of M1.

8.3 Females and Males of Reproductive Potential

Infertility

Use of opioids for an extended period of time may cause reduced fertility in females and males of reproductive potential. It is not known whether these effects on fertility are reversible [see Adverse Reactions (6.2)] .

Published studies in adult male rodents report that tramadol, at clinically relevant doses, can produce adverse effects on male reproductive hormones and tissues [See Nonclinical Toxicology (13.1)] .

8.4 Pediatric Use

The safety and effectiveness of tramadol in pediatric patients have not been established.

Life-threatening respiratory depression and death have occurred in children who received tramadol [see Warnings and Precautions (5.3)] . In some of the reported cases, these events followed tonsillectomy and/or adenoidectomy, and one of the children had evidence of being an ultra-rapid metabolizer of tramadol (i.e., multiple copies of the gene for cytochrome P450 isoenzyme 2D6). Children with sleep apnea may be particularly sensitive to the respiratory depressant effects of tramadol. Because of the risk of life-threatening respiratory depression and death:

- Tramadol hydrochloride oral solution is contraindicated for all children younger than 12 years of age [see Contraindications (4)] .
- Tramadol hydrochloride oral solution is contraindicated for postoperative management in pediatric patients younger than 18 years of age following tonsillectomy and/or adenoidectomy [see Contraindications (4)] .
- Avoid the use of tramadol hydrochloride oral solution in adolescents 12 to 18 years of age who have other risk factors that may increase their sensitivity to the respiratory depressant effects of tramadol unless the benefits outweigh the risks. Risk factors include conditions associated with hypoventilation such as postoperative status, obstructive sleep apnea, obesity, severe pulmonary disease, neuromuscular disease, and concomitant use of other medications that cause respiratory depression.

8.5 Geriatric Use

A total of 455 elderly (65 years of age or older) subjects were exposed to tramadol hydrochloride in controlled clinical trials. Of those, 145 subjects were 75 years of age and older.

In studies including geriatric patients, treatment-limiting adverse events were higher in subjects over 75 years of age compared to those under 65 years of age. Specifically, 30% of those over 75 years of age had gastrointestinal treatment-limiting adverse events compared to 17% of those under 65 years of age. Constipation resulted in discontinuation of treatment in 10% of those over 75.

Respiratory depression is the chief risk for elderly patients treated with opioids and has occurred after large initial doses were administered to patients who were not opioid-tolerant or when opioids were co-administered with other agents that depress respiration. Titrate the dosage of tramadol hydrochloride oral solution slowly in geriatric patients starting at the low end of the dosing range and frequently reevaluate the patient for signs of central nervous system and respiratory depression [see Warnings and Precautions (5.13)] .

Tramadol is known to be substantially excreted by the kidney, and the risk of adverse reactions to this drug may be greater in patients with impaired renal function. Because elderly patients are more likely to have decreased renal function, care should be taken in dose selection, and it may be useful to regularly evaluate renal function.

8.6 Renal and Hepatic Impairment

Impaired renal function results in a decreased rate and extent of excretion of tramadol and its active metabolite, M1. In patients with creatinine clearances of less than 30 mL/min, dosing reduction is recommended [see Dosage and Administration (2.3)] . Metabolism of tramadol and M1 is reduced in patients with severe hepatic impairment based on a study in patients with advanced cirrhosis of the liver. In patients with severe hepatic impairment, dosing reduction is recommended [see Dosage and Administration (2.3)] .

With the prolonged half-life in these conditions, achievement of steady-state is delayed, so that it may take several days for elevated plasma concentrations to develop.

9 DRUG ABUSE AND DEPENDENCE

9.1 Controlled Substance

Tramadol hydrochloride oral solution contains tramadol, a Schedule IV controlled substance.

9.2 Abuse

Tramadol hydrochloride oral solution contains tramadol, a substance with potential for misuse and abuse, which can lead to the development of substance use disorder, including addiction [see Warnings and Precautions (5.2)] .

Misuse is the intentional use, for therapeutic purposes, of a drug by an individual in a way other than prescribed by a health care provider or for whom it was not prescribed.

Abuse is the intentional, non-therapeutic use of a drug, even once, for its desirable psychological or physiological effects.

Drug addiction is a cluster of behavioral, cognitive, and physiological phenomena that may include a strong desire to take the drug, difficulties in controlling drug use (e.g., continuing drug use despite harmful consequences, giving a higher priority to drug use than other activities and obligations), and possible tolerance or physical dependence.

Misuse and abuse of tramadol hydrochloride oral solution increases risk of overdose, which may lead to central nervous system and respiratory depression, hypotension, seizures, and death. The risk is increased with concurrent abuse of tramadol hydrochloride oral solution with alcohol and/or other CNS depressants. Abuse of and addiction to opioids in some individuals may not be accompanied by concurrent tolerance and symptoms of physical dependence. In addition, abuse of opioids can occur in the absence of addiction.

All patients treated with opioids require careful and frequent reevaluation for signs of misuse, abuse, and addiction, because use of opioid analgesic products carries the risk of addiction even under appropriate medical use. Patients at high risk of tramadol hydrochloride oral solution abuse include those with a history of prolonged use of any opioid, including products containing tramadol, those with a history of drug or alcohol abuse, or those who use tramadol hydrochloride oral solution in combination with other abused drugs.

“Drug-seeking” behavior is very common in persons with substance use disorders. Drug-seeking tactics include emergency calls or visits near the end of office hours, refusal to undergo appropriate examination, testing, or referral, repeated “loss” of prescriptions, tampering with prescriptions, and reluctance to provide prior medical records or contact information for other treating healthcare provider(s). “Doctor shopping” (visiting multiple prescribers to obtain additional prescriptions) is common among people who abuse drugs and people with substance use disorder. Preoccupation with achieving adequate pain relief can be appropriate behavior in a patient with inadequate pain control.

Tramadol hydrochloride oral solution, like other opioids, can be diverted for nonmedical use into illicit channels of distribution. Careful record-keeping of prescribing information, including quantity, frequency, and renewal requests, as required by state and federal law, is strongly advised.

Proper assessment of the patient, proper prescribing practices, periodic reevaluation of therapy, and proper dispensing and storage are appropriate measures that help to limit abuse of opioid drugs.

Risks Specific to Abuse of Tramadol Hydrochloride Oral Solution

Abuse of tramadol hydrochloride oral solution poses a risk of overdose and death. The risk is increased with concurrent use of tramadol hydrochloride oral solution with alcohol and/or other CNS depressants.

Tramadol hydrochloride oral solution is approved for oral use only.

Parenteral drug abuse is commonly associated with transmission of infectious diseases such as hepatitis and HIV.

9.3 Dependence

Both tolerance and physical dependence can develop during use of opioid therapy.

Tolerance is a physiological state characterized by a reduced response to a drug after repeated administration (i.e., a higher dose of a drug is required to produce the same effect that was once obtained at a lower dose).

Physical dependence is a state that develops as a result of a physiological adaptation in response to repeated drug use, manifested by withdrawal signs and symptoms after abrupt discontinuation or a significant dose reduction of a drug.

Withdrawal may be precipitated through the administration of drugs with opioid antagonist activity (e.g., naloxone), mixed agonist/antagonist analgesics (e.g., pentazocine, butorphanol, nalbuphine), or partial agonists (e.g., buprenorphine). Physical dependence may not occur to a clinically significant degree until after several days to weeks of continued use.

Do not abruptly discontinue tramadol hydrochloride oral solution in a patient physically dependent on opioids. Rapid tapering of tramadol hydrochloride oral solution in a patient physically dependent on opioids may lead to serious withdrawal symptoms, uncontrolled pain, and suicide. Rapid discontinuation has also been associated with attempts to find other sources of opioid analgesics, which may be confused with drug seeking for abuse.

When discontinuing tramadol hydrochloride oral solution, gradually taper the dosage using a patient specific plan that considers the following: the dose of tramadol hydrochloride oral solution the patient has been taking, the duration of treatment, and the physical and psychological attributes of the patient. To improve the likelihood of a successful taper and minimize withdrawal symptoms, it is important that the opioid tapering schedule is agreed upon by the patient. In patients taking opioids for an extended period of time at high doses, ensure that a multimodal approach to pain management, including mental health support (if needed), is in place prior to initiating an opioid analgesic taper [see Dosage and Administration (2.5), and Warnings and Precautions (5.19)] .

Infants born to mothers physically dependent on opioids will also be physically dependent and may exhibit respiratory difficulties and withdrawal signs [see Use in Specific Populations (8.1)] .

10 OVERDOSAGE

Clinical Presentation

Acute overdosage with tramadol can be manifested by respiratory depression, somnolence progressing to stupor or coma, skeletal muscle flaccidity, cold and clammy skin, constricted pupils, and, in some cases, pulmonary edema, bradycardia, QT prolongation, hypotension, partial or complete airway obstruction, atypical snoring, seizures, and death. Marked mydriasis rather than miosis may be seen with hypoxia in overdose situations.

Deaths due to overdose have been reported with abuse and misuse of tramadol [see Warnings and Precautions (5.2), Drug Abuse and Dependence (9.2)] . Review of case reports has indicated that the risk of fatal overdose is further increased when tramadol is abused concurrently with alcohol or other CNS depressants, including other opioids.

Treatment of Overdose

In case of overdose, priorities are the re-establishment of a patent and protected airway and institution of assisted or controlled ventilation, if needed. Employ other supportive measures (including oxygen and vasopressors) in the management of circulatory shock and pulmonary edema as indicated. Cardiac arrest or serious arrhythmias will require advanced life-supporting measures.

Opioid antagonists, such as naloxone, are specific antidotes to respiratory depression resulting from opioid overdose. For clinically significant respiratory or circulatory depression secondary to tramadol overdose, administer an opioid antagonist.

While naloxone will reverse some, but not all, symptoms caused by overdosage with tramadol, the risk of seizures is also increased with naloxone administration. In animals, convulsions following the administration of toxic doses of tramadol hydrochloride could be suppressed with barbiturates or benzodiazepines but were increased with naloxone. Naloxone administration did not change the lethality of an overdose in mice. Hemodialysis is not expected to be helpful in an overdose because it removes less than 7% of the administered dose in a 4-hour dialysis period.

Because the duration of opioid reversal is expected to be less than the duration of action of tramadol in tramadol hydrochloride oral solution, carefully monitor the patient until spontaneous respiration is reliably re-established. If the response to an opioid antagonist is suboptimal or only brief in nature, administer additional antagonist as directed by the product's prescribing information.

In an individual physically dependent on opioids, administration of the recommended usual dosage of the antagonist will precipitate an acute withdrawal syndrome. The severity of the withdrawal symptoms experienced will depend on the degree of physical dependence and the dose of the antagonist administered. If a decision is made to treat serious respiratory depression in the physically dependent patient, administration of the antagonist should be begun with care and by titration with smaller than usual doses of the antagonist.

11 DESCRIPTION

Tramadol hydrochloride oral solution is an opioid agonist. The chemical name for tramadol hydrochloride is (±) cis-2-[(dimethylamino)methyl]-1-(3-methoxyphenyl) cyclohexanol hydrochloride. The structural formula is:

The molecular formula of tramadol hydrochloride is C16H25NO2 · HCl, and the molecular weight is 299.8. Tramadol hydrochloride is a white, bitter, crystalline and odorless powder. It is readily soluble in water and ethanol and has a pKa of 9.41. The n-octanol/water log partition coefficient (logP) is 1.35 at pH 7. Tramadol hydrochloride oral solution is a clear, grape flavored liquid containing 5 mg of tramadol hydrochloride per 1 mL (equivalent to tramadol 4.4 mg per 1 mL)

Inactive ingredients include: citric acid, glycerin, grape flavor, propylene glycol, purified water, sodium benzoate, sodium citrate dihydrate, and sucralose.

12 CLINICAL PHARMACOLOGY

12.1 Mechanism of Action

Tramadol hydrochloride oral solution contains tramadol, an opioid agonist and inhibitor of norepinephrine and serotonin re-uptake. Although the mode of action is not completely understood, the analgesic effect of tramadol is believed to be due to both binding to µ-opioid receptors and weak inhibition of re-uptake of norepinephrine and serotonin.

Opioid activity is due to both low affinity binding of the parent compound and higher affinity binding of the O-demethylated metabolite M1 to µ-opioid receptors. In animal models, M1 is up to 6 times more potent than tramadol in producing analgesia and 200 times more potent in µ-opioid binding. Tramadol-induced analgesia is only partially antagonized by the opioid antagonist naloxone in several animal tests. The relative contribution of both tramadol and M1 to human analgesia is dependent upon the plasma concentrations of each compound [see Clinical Pharmacology (12.2)] .

Analgesia in humans begins approximately within one hour after administration and reaches a peak in approximately two to three hours.

12.2 Pharmacodynamics

Effects on the Central Nervous System

Tramadol produces respiratory depression by direct action on brain stem respiratory centers. The respiratory depression involves a reduction in the responsiveness of the brain stem respiratory centers to both increases in carbon dioxide tension and electrical stimulation.

Tramadol administration may produce a constellation of symptoms including nausea and vomiting, dizziness, and somnolence.

Tramadol causes miosis, even in total darkness. Pinpoint pupils are a sign of opioid overdose but are not pathognomonic (e.g., pontine lesions of hemorrhagic or ischemic origins may produce similar findings). Marked mydriasis rather than miosis may be seen due to hypoxia in overdose situations.

Effects on the Gastrointestinal Tract and Other Smooth Muscle

Tramadol causes a reduction in motility associated with an increase in smooth muscle tone in the antrum of the stomach and duodenum. Digestion of food in the small intestine is delayed and propulsive contractions are decreased. Propulsive peristaltic waves in the colon are decreased, while tone may be increased to the point of spasm resulting in constipation. Other opioid-induced effects may include a reduction in biliary and pancreatic secretions, spasm of sphincter of Oddi, and transient elevations in serum amylase.

Effects on the Cardiovascular System

Tramadol produces peripheral vasodilation, which may result in orthostatic hypotension or syncope. Manifestations of peripheral vasodilation may include pruritus, flushing, red eyes, sweating and/or orthostatic hypotension.

The effect of oral tramadol on the QTcF interval was evaluated in a double-blind, randomized, four-way crossover, placebo- and positive- (moxifloxacin) controlled study in 68 adult male and female healthy subjects. At a 600 mg/day dose (1.5-fold the maximum immediate-release daily dose), the study demonstrated no significant effect on the QTcF interval.

Effects on the Endocrine System

Opioids inhibit the secretion of adrenocorticotropic hormone (ACTH), cortisol, and luteinizing hormone (LH) in humans. They also stimulate prolactin, growth hormone (GH) secretion, and pancreatic secretion of insulin and glucagon [see Warnings and Precautions (5.14); Adverse Reactions (6)] .

Use of opioids for an extended period of time may influence the hypothalamic-pituitary-gonadal axis, leading to androgen deficiency that may manifest as low libido, impotence, erectile dysfunction, amenorrhea, or infertility. The causal role of opioids in the clinical syndrome of hypogonadism is unknown because the various medical, physical, lifestyle, and psychological stressors that may influence gonadal hormone levels have not been adequately controlled for in studies conducted to date [see Adverse Reactions (6)] .

Effects on the Immune System

Opioids have been shown to have a variety of effects on components of the immune system in in vitroand animal models. The clinical significance of these findings is unknown. Overall, the effects of opioids appear to be modestly immunosuppressive.

Concentration–Efficacy Relationships

The minimum effective analgesic concentration will vary widely among patients, especially among patients who have been previously treated with opioid agonists. The minimum effective analgesic concentration of tramadol for any individual patient may increase over time due to an increase in pain, the development of a new pain syndrome and/or the development of analgesic tolerance [see Dosage and Administration (2.1, 2.4)] .

Concentration–Adverse Reaction Relationships

There is a relationship between increasing tramadol plasma concentration and increasing frequency of dose-related opioid adverse reactions such as nausea, vomiting, CNS effects, and respiratory depression. In opioid-tolerant patients, the situation may be altered by the development of tolerance to opioid-related adverse reactions [see Dosage and Administration (2.1, 2.4)] .

12.3 Pharmacokinetics

The analgesic activity of tramadol hydrochloride oral solution is due to both parent drug and the M1 metabolite [see Clinical Pharmacology (12.1, 12.2)] . Tramadol is administered as a racemate and both the [-] and [+] forms of both tramadol and M1 are detected in the circulation. Linear pharmacokinetics have been observed following multiple doses of 50 and 100 mg to steady-state.

Absorption

Table 3shows the mean plasma concentrations of tramadol and M1 pharmacokinetic parameters following a single-dose administration of 50 mg tramadol hydrochloride oral solution and 50 mg immediate-release tramadol tablet under fasted conditions in healthy adult subjects.

Table 3: Summary of Tramadol and M1 Pharmacokinetic Parameters Following Single Dose Administration Under Fasted Condition in Healthy Adult Subjects
Parameters | Tramadol Hydrochloride Oral Solution 50 mg Fasted | Immediate-release tramadol tablet 50 mg Fasted | Tramadol Hydrochloride Oral Solution 50 mg Fasted | Immediate-release tramadol tablet 50 mg Fasted
Parameters | Tramadol |  | M1
Parameters | Mean ± SD | Mean ± SD | Mean ± SD | Mean ± SD
Tmax [median (min – max)] (hr) | 1.5 (0.50 2.50) | 1.5 (0.75 3.0) | 2.0 (0.50 5.00) | 2.25 (1.25 10.00)
Cmax(ng/mL) | 180.20 ± 33.81 | 173.51 ± 29.59 | 47.77 ± 19.06 | 46.14 ± 18.28
AUC0-t(hr*ng/mL) | 1623.93 ± 502.43 | 1681.64 ± 578.06 | 624.12 ± 205.58 | 624.10 ± 199.82
AUC0-inf(hr*ng/mL) | 1658.31 ± 525.97 | 1721.47 ± 624.72 | 638.95 ± 207.13 | 639.26 ± 198.04
t1/2(hr) | 7.65 ± 1.63 | 7.61 ± 1.82 | 7.94 ± 1.65 | 8.06 ± 2.11

The mean absolute bioavailability of a 100 mg oral dose is approximately 75%. The mean peak plasma concentration of racemic tramadol and M1 occurs at two and three hours, respectively, after administration in healthy adults. In general, both enantiomers of tramadol and M1 follow a parallel time course in the body following single and multiple doses although small differences (~ 10%) exist in the absolute amount of each enantiomer present.

Steady-state plasma concentrations of both tramadol and M1 are achieved within two days with four-times-per-day dosing. There is no evidence of self-induction (see Figure 1and Table 4below).

Figure 1: Mean Tramadol and M1 Plasma Concentration Profiles after a Single 100 mg Oral Dose and after Twenty-Nine 100 mg Oral Doses of Tramadol HCl given four times per day.

Table 4: Mean (%CV) Pharmacokinetic Parameters for Racemic Tramadol and M1 Metabolite
Population/Dosage Regimen [SD = Single dose, MD = Multiple dose, p.o.= Oral administration, i.v.= Intravenous administration, q.i.d. = Four times daily] | Parent Drug/ Metabolite | Peak Conc.(ng/mL) | Time to Peak (hrs) | Clearance/F b [F represents the oral bioavailability of tramadol] (mL/min/Kg) | t1/2(hrs)
Healthy Adults, 100 mg qid, MD p.o. | Tramadol M1 | 592 (30) 110 (29) | 2.3 (61) 2.4 (46) | 5.90 (25) [Not applicable] | 6.7 (15) 7.0 (14)
Healthy Adults, 100 mg SD p.o. | Tramadol M1 | 308 (25) 55.0 (36) | 1.6 (63) 3.0 (51) | 8.50 (31) | 5.6 (20) 6.7 (16)
Geriatric, (>75 yrs) 50 mg SD p.o. | Tramadol M1 | 208 (31) [Not measured] | 2.1 (19) | 6.89 (25) | 7.0 (23)
Hepatic Impaired, 50 mg SD p.o. | Tramadol M1 | 217 (11) 19.4 (12) | 1.9 (16) 9.8 (20) | 4.23 (56) | 13.3 (11) 18.5 (15)
Renal Impaired, CLcr1030 mL/min 100 mg SD i.v. | Tramadol M1 |  |  | 4.23 (54) | 10.6 (31) 11.5 (40)
Renal Impaired, CLcr<5 mL/min 100 mg SD i.v. | Tramadol M1 |  |  | 3.73 (17) | 11.0 (29) 16.9 (18)

Food Effects

Oral administration of tramadol hydrochloride oral solution with food does not significantly affect its rate or extent of absorption, therefore, tramadol hydrochloride oral solution can be administered without regard to food.

Distribution

The volume of distribution of tramadol was 2.6 and 2.9 liters/kg in male and female subjects, respectively, following a 100 mg intravenous dose. The binding of tramadol to human plasma proteins is approximately 20% and binding also appears to be independent of concentration up to 10 mcg/mL. Saturation of plasma protein binding occurs only at concentrations outside the clinically relevant range.

Elimination

Tramadol is eliminated primarily through metabolism by the liver and the metabolites are eliminated primarily by the kidneys. The mean (%CV) apparent total clearance of tramadol after a single 100 mg oral dose is 8.50 (31) mL/min/kg. The mean terminal plasma elimination half-lives of racemic tramadol and racemic M1 are 6.3 ± 1.4 and 7.4 ± 1.4 hours, respectively. The plasma elimination half-life of racemic tramadol increased from approximately six hours to seven hours upon multiple dosing.

Metabolism

Tramadol is extensively metabolized after oral administration by a number of pathways, including CYP2D6 and CYP3A4, as well as by conjugation of parent and metabolites. Approximately 30% of the dose is excreted in the urine as unchanged drug, whereas 60% of the dose is excreted as metabolites. The remainder is excreted either as unidentified or as unextractable metabolites. The major metabolic pathways appear to be N- and O-demethylation and glucuronidation or sulfation in the liver. One metabolite (O-desmethyltramadol, denoted M1) is pharmacologically active in animal models. Formation of M1 is dependent on CYP2D6 and as such is subject to inhibition, which may affect the therapeutic response [Warnings and Precautions (5.7); Drug Interactions (7)] .

Approximately 7% of the population has reduced activity of the CYP2D6 isoenzyme of cytochrome P-450. These individuals are "poor metabolizers" of debrisoquine, dextromethorphan, tricyclic antidepressants, among other drugs. Based on a population PK analysis of Phase I studies in healthy subjects, concentrations of tramadol were approximately 20% higher in "poor metabolizers" versus "extensive metabolizers", while M1 concentrations were 40% lower. Concomitant therapy with inhibitors of CYP2D6 such as fluoxetine, paroxetine and quinidine could result in significant drug interactions. In vitrodrug interaction studies in human liver microsomes indicate that inhibitors of CYP2D6 such as fluoxetine and its metabolite norfluoxetine, amitriptyline and quinidine inhibit the metabolism of tramadol to various degrees, suggesting that concomitant administration of these compounds could result in increases in tramadol concentrations and decreased concentrations of M1. The full pharmacological impact of these alterations in terms of either efficacy or safety is unknown. Concomitant use of serotonin re-uptake inhibitors and MAO inhibitors may enhance the risk of adverse events, including seizure and serotonin syndrome [see Warnings and Precautions (5.10), Drug Interactions (7)] .

Excretion

Tramadol metabolites are eliminated primarily by the kidneys. Approximately 30% of the dose is excreted in the urine as unchanged drug, whereas 60% of the dose is excreted as metabolites. The remainder is excreted either as unidentified or as unextractable metabolites.

Special Populations

Hepatic Impairment

Metabolism of tramadol and M1 is reduced in patients with severe hepatic impairment based on a study in patients with advanced cirrhosis of the liver, resulting in both a larger area under the concentration time curve for tramadol and longer tramadol and M1 elimination half-lives (13 hrs. for tramadol and 19 hrs. for M1). In patients with severe hepatic impairment, adjustment of the dosing regimen is recommended [see Dosage and Administration (2)] .

Renal Impairment

Impaired renal function results in a decreased rate and extent of excretion of tramadol and its active metabolite, M1. In patients with creatinine clearances of less than 30 mL/min, adjustment of the dosing regimen is recommended [see Dosage and Administration (2)] . The total amount of tramadol and M1 removed during a 4-hour dialysis period is less than 7% of the administered dose.

Age: Geriatric

Healthy elderly subjects aged 65 to 75 years have plasma tramadol concentrations and elimination half-lives comparable to those observed in healthy subjects less than 65 years of age. In subjects over 75 years, maximum serum concentrations are elevated (208 vs. 162 ng/mL) and the elimination half-life is prolonged (7 vs. 6 hours) compared to subjects 65 to 75 years of age. Adjustment of the daily dose is recommended for patients older than 75 years [see Dosage and Administration (2.3)] .

Sex

The absolute bioavailability of tramadol was 73% in males and 79% in females. The plasma clearance was 6.4 mL/min/kg in males and 5.7 mL/min/kg in females following a 100 mg IV dose of tramadol. Following a single oral dose, and after adjusting for body weight, females had a 12% higher peak tramadol concentration and a 35% higher area under the concentration-time curve compared to males. The clinical significance of this difference is unknown.

Poor / Extensive Metabolizers, CYP2D6

The formation of the active metabolite, M1, is mediated by CYP2D6, a polymorphic enzyme. Approximately 7% of the population has reduced activity of the CYP2D6 isoenzyme of cytochrome P450 metabolizing enzyme system. These individuals are "poor metabolizers" of debrisoquine, dextromethorphan and tricyclic antidepressants, among other drugs. Based on a population PK analysis of Phase 1 studies with IR tablets in healthy subjects, concentrations of tramadol were approximately 20% higher in "poor metabolizers" versus "extensive metabolizers," while M1 concentrations were 40% lower.

13 NONCLINICAL TOXICOLOGY

13.1 Carcinogenesis, Mutagenesis, Impairment of Fertility

Carcinogenesis

A slight, but statistically significant, increase in two common murine tumors, pulmonary and hepatic, was observed in an NMRI mouse carcinogenicity study, particularly in aged mice. Mice were dosed orally up to 30 mg/kg in the drinking water (0.36 times the MRHD) for approximately two years, although the study was not done with the Maximum Tolerated Dose. This finding is not believed to suggest risk in humans. No evidence of carcinogenicity was noted in a rat 2-year carcinogenicity study testing oral doses of up to 30 mg/kg in the drinking water, 0.73 times the MRHD.

Mutagenesis

Tramadol was mutagenic in the presence of metabolic activation in the mouse lymphoma assay. Tramadol was not mutagenic in the in vitrobacterial reverse mutation assay using Salmonellaand E. coli(Ames), the mouse lymphoma assay in the absence of metabolic activation, the in vitrochromosomal aberration assay, or the in vivomicronucleus assay in bone marrow.

Impairment of Fertility

No effects on fertility were observed for tramadol at oral dose levels up to 50 mg/kg in male rats and 75 mg/kg in female rats. These dosages are 1.2 and 1.8 times the maximum recommended human daily dose based on body surface area, respectively.

However, published studies report that treatment of adult male rats with tramadol (40 mg/kg, IP and SC for 30 and 60 days, respectively, 1.2x the MRHD based on BSA; or 4.5 to 135 mg/kg, SC for 18 weeks, 0.01x to 3.2x the MRHD based on BSA) produced adverse effects on male reproductive hormones and male reproductive tissues.

14 CLINICAL STUDIES

Tramadol hydrochloride has been given in single oral doses of 50, 75 and 100 mg to patients with pain following surgical procedures and pain following oral surgery (extraction of impacted molars).

In single-dose models of pain following oral surgery, pain relief was demonstrated in some patients at doses of 50 mg and 75 mg. A dose of 100 mg tramadol hydrochloride tended to provide analgesia superior to codeine sulfate 60 mg, but it was not as effective as the combination of aspirin 650 mg with codeine phosphate 60 mg.

Tramadol hydrochloride has been studied in three long-term controlled trials involving a total of 820 patients, with 530 patients receiving tramadol hydrochloride. Patients with a variety of chronic painful conditions were studied in double-blind trials of one to three months duration. Average daily doses of approximately 250 mg of tramadol hydrochloride in divided doses were generally comparable to five doses of acetaminophen 300 mg with codeine phosphate 30 mg (TYLENOL with Codeine #3) daily, five doses of aspirin 325 mg with codeine phosphate 30 mg daily, or two to three doses of acetaminophen 500 mg with oxycodone hydrochloride 5 mg (TYLOX) daily.

Titration Trials

In a randomized, blinded clinical study with 129 to 132 patients per group, a 10-day titration to a daily tramadol hydrochloride dose of 200 mg (50 mg four times per day), attained in 50 mg increments every 3 days, was found to result in fewer discontinuations due to dizziness or vertigo than titration over only 4 days or no titration. In a second study with 54 to 59 patients per group, patients who had nausea or vomiting when titrated over 4 days were randomized to re-initiate tramadol hydrochloride therapy using slower titration rates.

A 16-day titration schedule, starting with 25 mg every morning and using additional doses in 25 mg increments every third day to 100 mg/day (25 mg four times per day), followed by 50 mg increments in the total daily dose every third day to 200 mg/day (50 mg four times per day), resulted in fewer discontinuations due to nausea or vomiting and fewer discontinuations due to any cause than did a 10-day titration schedule (See Figure 2).

Figure 2:

16 HOW SUPPLIED/STORAGE AND HANDLING

Tramadol hydrochloride oral solution is supplied as a clear, grape flavored liquid containing tramadol HCl, 5 mg/mL.
Supplied in:

NDC 68134-402-05: 5 mL unit dose cup

NDC 68134-402-40: Case containing 40 unit dose cups of 5 mL (68134-402-05)

STORAGE AND HANDLING

Dispense in a tight container. Store at 20°C to 25°C (68°F to 77°F); excursions permitted to 15°C to30°C (59°F to 86°F). [see USP Controlled Room Temperature].

Store tramadol hydrochloride oral solution securely and dispose of properly [see Patient Counseling Information (17)].

17 PATIENT COUNSELING INFORMATION

Advise the patient to read the FDA-approved patient labeling (Medication Guide).

Storage and Disposal

Because of the risks associated with accidental ingestion, misuse, and abuse, advise patients to store tramadol hydrochloride oral solution securely, out of sight and reach of children, and in a location not accessible by others, including visitors to the home. Inform patients that leaving tramadol hydrochloride oral solution unsecured can pose a deadly risk to others in the home [see Warnings and Precautions (5.2, 5.3), Drug Abuse and Dependence (9.2)] .

Advise patients and caregivers that when medicines are no longer needed, they should be disposed of promptly. Inform patients that medicine take-back options are the preferred way to safely dispose of most types of unneeded medicines. If no take back programs or Drug Enforcement Administration (DEA)-registered collectors are available, instruct patients to dispose of tramadol hydrochloride oral solution by following these four steps:

- Mix tramadol hydrochloride oral solution with an unpalatable substance such as dirt, cat litter, or used coffee grounds;
- Place the mixture in a container such as a sealed plastic bag;
- Throw the container in the household trash;
- Remove all personal information on the prescription label of the empty bottle.

Inform patients that they can visit www.fda.gov/drugdisposal for additional information on disposal of unused medicines.

Medication Errors

Strongly advise patients and caregivers to always use a graduated oral syringe or measuring cup, with metric units of measurements (i.e., mL), to correctly measure the prescribed amount of medication.

Inform patients that oral dosing devices may be obtained from their pharmacy and to never use household teaspoons or tablespoons to measure tramadol hydrochloride oral solution [see Dosage and Administration (2.1), Warnings and Precautions (5.1)] .

Addiction, Abuse, and Misuse

Inform patients that the use of tramadol hydrochloride oral solution, even when taken as recommended, can result in addiction, abuse, and misuse, which can lead to overdose and death [see Warnings and Precautions (5.2)] . Instruct patients not to share tramadol hydrochloride oral solution with others and to take steps to protect tramadol hydrochloride oral solution from theft or misuse.

Life-Threatening Respiratory Depression

Inform patients of the risk of life-threatening respiratory depression, including information that the risk is greatest when starting tramadol hydrochloride oral solution or when the dosage is increased, and that it can occur even at recommended dosages. Educate patients and caregivers on how to recognize respiratory depression and emphasize the importance of calling 911 or getting emergency medical help right away in the event of a known or suspected overdose [see Warnings and Precautions (5.3)] .

Accidental Ingestion

Inform patients that accidental ingestion, especially by children, may result in respiratory depression or death [see Warnings and Precautions (5.3)] .

Interactions with Benzodiazepines and Other CNS Depressants

Inform patients and caregivers that potentially fatal additive effects may occur if tramadol hydrochloride oral solution is used with benzodiazepines, CNS depressants, including alcohol, or some illicit drugs and not to use these concomitantly unless supervised by a healthcare provider [see Warnings and Precautions (5.4), Drug Interactions (7)] .

Patient Access to Naloxone for the Emergency Treatment of Opioid Overdose

Discuss with the patient and caregiver the availability of naloxone for the emergency treatment of opioid overdose, both when initiating and renewing treatment with tramadol hydrochloride oral solution. Inform patients and caregivers about the various ways to obtain naloxone as permitted by individual state naloxone dispensing and prescribing requirements or guidelines (e.g., by prescription, directly from a pharmacist, or as part of a community-based program) [see Dosage and Administration (2.2), Warnings and Precautions (5.3)] .

Educate patients and caregivers on how to recognize the signs and symptoms of an overdose.

Explain to patients and caregivers that naloxone’s effects are temporary, and that they must call 911 or get emergency medical help right away in all cases of known or suspected opioid overdose, even if naloxone is administered [see Overdosage (10)] .

If naloxone is prescribed, also advise patients and caregivers:

- How to treat with naloxone in the event of an opioid overdose
- To tell family and friends about their naloxone and to keep it in a place where family and friends can access it in an emergency
- To read the Patient Information (or other educational material) that will come with their naloxone. Emphasize the importance of doing this before an opioid emergency happens, so the patient and caregiver will know what to do.

Ultra-Rapid Metabolism of Tramadol and Other Risk Factors for Life-threatening Respiratory Depression in Children

Advise caregivers that tramadol hydrochloride oral solution is contraindicated in children younger than 12 years of age and in children younger than 18 years of age following tonsillectomy and/or adenoidectomy. Advise caregivers of children ages 12 to 18 years of age receiving tramadol hydrochloride oral solution to monitor for signs of respiratory depression [see Warnings and Precautions (5.7)] .

Hyperalgesia and Allodynia

Inform patients and caregivers not to increase opioid dosage without first consulting a clinician. Advise patients to seek medical attention if they experience symptoms of hyperalgesia, including worsening pain, increased sensitivity to pain, or new pain [see Warnings and Precautions (5.9), Adverse Reactions (6.2)] .

Maximum single-dose and 24-hour dose

Advise patients not to exceed the single-dose and 24-hour dose limit and the time interval between doses, since exceeding these recommendations can result in respiratory depression, seizures and death [see Dosage and Administration (2), Warnings and Precautions (5.3)] .

Serotonin Syndrome

Inform patients that opioids could cause a rare but potentially life-threatening condition resulting from concomitant administration of serotonergic drugs. Warn patients of the symptoms of serotonin syndrome, and to seek medical attention right away if symptoms develop. Instruct patients to inform their healthcare provider if they are taking, or plan to take serotonergic medications [see Warnings and Precautions (5.10)] .

Seizures

Inform patients that tramadol hydrochloride oral solution may cause seizures with concomitant use of serotonergic agents (including SSRIs, SNRIs, and triptans) or drugs that significantly reduce the metabolic clearance of tramadol [see Warnings and Precautions (5.11)] .

MAOI Interaction

Inform patients not to take tramadol hydrochloride oral solution while using any drugs that inhibit monoamine oxidase. Patients should not start MAOIs while taking tramadol hydrochloride oral solution [see Drug Interactions (7)] .

Important Administration Instructions

- Instruct patients and caregivers on how to measure and take or administer the correct dose of tramadol hydrochloride oral solution.
- Strongly advise patients and caregivers to always use a graduated oral syringe or other oral dosing device, with metric units of measurements (i.e., mL), to correctly measure the prescribed amount of medication.
- Inform patients and caregivers that oral dosing devices may be obtained from their pharmacy and to never use household teaspoons or tablespoons to measure tramadol hydrochloride oral solution [see Dosage and Administration (2.1)] .
- Advise patients and caregivers not to adjust the dose of tramadol hydrochloride oral solution without consulting with a physician or other healthcare professional.

Important Discontinuation Instructions

In order to avoid developing withdrawal symptoms, instruct patients not to discontinue tramadol hydrochloride oral solution without first discussing a tapering plan with the prescriber [see Dosage and Administration (2.5)] .

Driving or Operating Heavy Machinery

Inform patients that tramadol hydrochloride oral solution may impair the ability to perform potentially hazardous activities such as driving a car or operating heavy machinery. Advise patients not to perform such tasks until they know how they will react to the medication [see Warnings and Precautions (5.20)] .

Constipation

Advise patients of the potential for severe constipation, including management instructions and when to seek medical attention [see Adverse Reactions (6)] .

Adrenal Insufficiency

Inform patients that opioids could cause adrenal insufficiency, a potentially life-threatening condition. Adrenal insufficiency may present with non-specific symptoms and signs such as nausea, vomiting, anorexia, fatigue, weakness, dizziness, and low blood pressure. Advise patients to seek medical attention if they experience a constellation of these symptoms [see Warnings and Precautions (5.14)] .

Hypotension

Inform patients that tramadol hydrochloride oral solution may cause orthostatic hypotension and syncope. Instruct patients how to recognize symptoms of low blood pressure and how to reduce the risk of serious consequences should hypotension occur (e.g., sit or lie down, carefully rise from a sitting or lying position) [see Warnings and Precautions (5.15)] .

Anaphylaxis

Inform patients that anaphylaxis has been reported with ingredients contained in tramadol hydrochloride oral solution. Advise patients how to recognize such a reaction and when to seek medical attention [see Contraindications (4), Warnings and Precautions (5.18), Adverse Reactions (6)] .

Pregnancy

Neonatal Opioid Withdrawal Syndrome

Inform female patients of reproductive potential that use of tramadol hydrochloride oral solution for an extended period of time during pregnancy can result in neonatal opioid withdrawal syndrome, which may be life-threatening if not recognized and treated and that the patient should inform their healthcare provider if they have used opioids at any time during their pregnancy, especially near the time of birth. [see Warnings and Precautions (5.5), Use in Specific Populations (8.1)] .

Embryo-Fetal Toxicity

Inform female patients of reproductive potential that tramadol hydrochloride oral solution may cause fetal harm and to inform the healthcare provider of a known or suspected pregnancy [see Use in Specific Populations (8.1)] .

Lactation

Advise women that breastfeeding is not recommended during treatment with tramadol hydrochloride oral solution [see Warnings and Precautions (5.5), Use in Specific Populations (8.2)] .

Infertility

Inform patients that use of opioids for an extended period of time may cause reduced fertility. It is not known whether these effects on fertility are reversible [see Use in Specific Populations (8.3)] .

Distributed by:
Palmetto Pharmaceuticals, Inc.
Greenville, SC 29615

Revised 12/2023
500529-02

MEDICATION GUIDE
Tramadol Hydrochloride Oral Solution, CIV

Tramadol hydrochloride oral solution is:

- A strong prescription pain medicine that contains an opioid (narcotic) that is used for the management of pain in adults, when other pain treatments such as non-opioid pain medicines do not treat your pain well enough or you cannot tolerate them.
- An opioid pain medicine that can put you at risk for overdose and death. Even if you take your dose correctly as prescribed you are at risk for opioid addiction, abuse, and misuse that can lead to death.

Important information about tramadol hydrochloride oral solution:

- Get emergency help right away if you take too much tramadol hydrochloride oral solution (overdose). When you first start taking tramadol hydrochloride oral solution, when your dose is changed, or if you take too much (overdose), serious or life-threatening breathing problems that can lead to death may occur.
- Taking tramadol hydrochloride oral solution with other opioid medicines, benzodiazepines, alcohol, or other central nervous system depressants (including street drugs) can cause severe drowsiness, decreased awareness, breathing problems, coma, and death.
- Never give anyone else your tramadol hydrochloride oral solution. They could die from taking it. Selling or giving away tramadol hydrochloride oral solution is against the law.
- Store tramadol hydrochloride oral solution securely, out of sight and reach of children, and in a location not accessible by others, including visitors to the home.

Important Information Guiding Use in Pediatric Patients:

- Do not give tramadol hydrochloride oral solution to a child younger than 12 years of age.
- Do not give tramadol hydrochloride oral solution to anyone younger than 18 years of age after surgery to remove the tonsils, adenoids, or both.
- Avoid giving tramadol hydrochloride oral solution to children between 12 to 18 years of age who have risk factors for breathing problems such as obstructive sleep apnea, obesity, or underlying lung problems.

Do not take tramadol hydrochloride oral solution if you have:

- Severe asthma, trouble breathing, or other lung problems.
- A bowel blockage or have narrowing of the stomach or intestines.
- An allergy to tramadol.
- Taken a Monoamine Oxidase Inhibitor, MAOI, (medicine used for depression) within the last 14 days.

Before taking tramadol hydrochloride oral solution, tell your healthcare provider if you have a history of:

- head injury, seizures
- problems urinating
- abuse of street or prescription drugs, alcohol addiction, or mental health problems.

- liver, kidney, thyroid problems
- pancreas or gallbladder problems

Tell your healthcare provider if you are:

- noticing your pain getting worse. If your pain gets worse after you take tramadol hydrochloride oral solution, do not take more of tramadol hydrochloride oral solution without first talking to your healthcare provider. Talk to your healthcare provider if the pain that you have increases, if you feel more sensitive to pain, or if you have new pain after taking tramadol hydrochloride oral solution.
- pregnant or planning to become pregnant. Use of tramadol hydrochloride oral solution for an extended period of time during pregnancy can cause withdrawal symptoms in your newborn baby that could be life-threatening if not recognized and treated.
- breastfeeding. Not recommended during treatment with tramadol hydrochloride oral solution; it may harm your baby.
- taking prescription or over-the-counter medicines, vitamins, or herbal supplements. Taking tramadol hydrochloride oral solution with certain other medicines can cause serious side effects that could lead to death.

When taking tramadol hydrochloride oral solution:

- Do not change your dose. Take tramadol hydrochloride oral solution exactly as prescribed by your healthcare provider. Use the lowest dose possible for the shortest time needed.
- For acute (short-term) pain, you may only need to take tramadol hydrochloride oral solution for a few days. You may have some tramadol hydrochloride oral solution left over that you did not use. See disposal information at the bottom of this section for directions on how to safely throw away (dispose of) your unused tramadol hydrochloride oral solution.
- Always use a calibrated oral syringe or other oral dosing device obtained from your doctor or pharmacist to
  correctly measure your dose. Never use a household teaspoon or tablespoon to measure tramadol hydrochloride oral solution.
- Take your prescribed dose as indicated by your healthcare provider. The maximum dosage is 10 mL to 20 mL every 4 to 6 hours, as needed for pain. Do not take more than your prescribed dose and do not take more than 80 mL per day. If you miss a dose, take your next dose at your usual time.
- Call your healthcare provider if the dose you are taking does not control your pain.
- If you have been taking tramadol hydrochloride oral solution regularly, do not stop taking tramadol hydrochloride oral solution without talking to your healthcare provider.
- Dispose of expired, unwanted, or unused tramadol hydrochloride oral solution by taking your drug to an authorized Drug Enforcement
  Administration (DEA)-registered collector or drug take-back program. If one is not available, you can dispose of
  tramadol hydrochloride oral solution by mixing tramadol hydrochloride oral solution with dirt, cat litter, or used coffee grounds; placing the mixture in a container such as a
  sealed plastic bag; and throwing the container in the household trash. Visit www.fda.gov/drugdisposalfor additional information on disposal of unused medicines.

While taking tramadol hydrochloride oral solution DO NOT:

- Drive or operate heavy machinery, until you know how tramadol hydrochloride oral solution affects you. Tramadol hydrochloride oral solution can make you sleepy, dizzy, or lightheaded.
- Drink alcohol or use prescription or over-the-counter medicines that contain alcohol. Using products containing alcohol during treatment with tramadol hydrochloride oral solution may cause you to overdose and die.

The possible side effects of tramadol hydrochloride oral solution:

- constipation, nausea, sleepiness, vomiting, tiredness, headache, dizziness, abdominal pain. Call your healthcare provider if you have any of these symptoms and they are severe.

Get emergency medical help if you have:

- trouble breathing, shortness of breath, fast heartbeat, chest pain, swelling of your face, tongue, or throat, extreme drowsiness, light-headedness when changing positions, feeling faint, agitation, high body temperature, trouble walking, stiff muscles, or mental changes such as confusion.

These are not all the possible side effects of tramadol hydrochloride oral solution. Call your healthcare provider for medical advice about side effects. You may report side effects to FDA at 1-800-FDA-1088. For more information go to dailymed.nlm.nih.gov.

Distributed by: Palmetto Pharmaceuticals, Inc., Greenville, SC 29615 .
This Medication Guide has been approved by the U.S. Food and Drug Administration. Issued/Revised: 12/2023

PRINCIPAL DISPLAY PANEL - Tramadol hydrochloride oral solution 5 mg/mL, 5 mL Unit Dose Cup

NDC 68134-402-05

Tramadol hydrochloride oral solution 5 mg/mL (equivalent to tramadol 4.4 mg per 1 mL) CIV

Keep out of reach of children.

Rx only

5 mL unit dose cup

PRINCIPAL DISPLAY PANEL - Tramadol hydrochloride oral solution 5 mg/mL, case containing 40 5 mL Unit Dose Cup

NDC 68134-402-40

Tramadol hydrochloride oral solution 5 mg/mL (equivalent to tramadol 4.4 mg per 1 mL) CIV

Keep out of reach of children.

Rx only

Case containing 40 unit dose cups